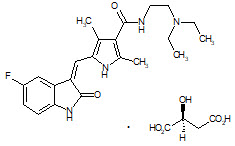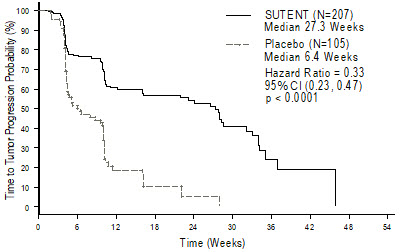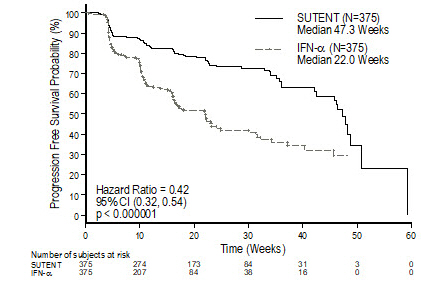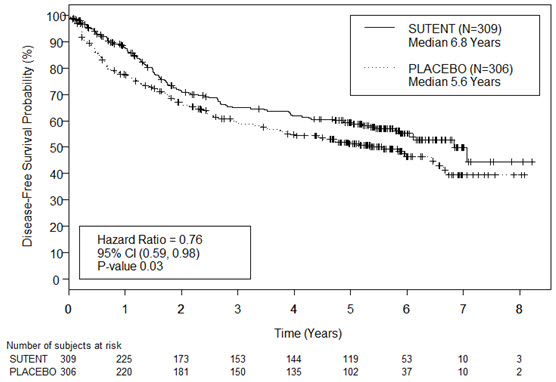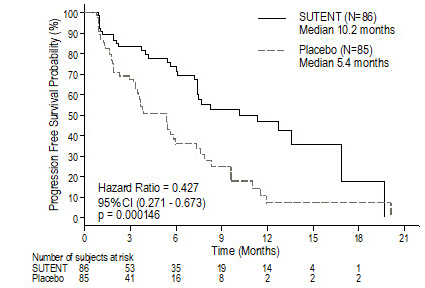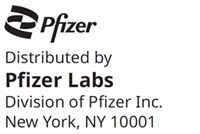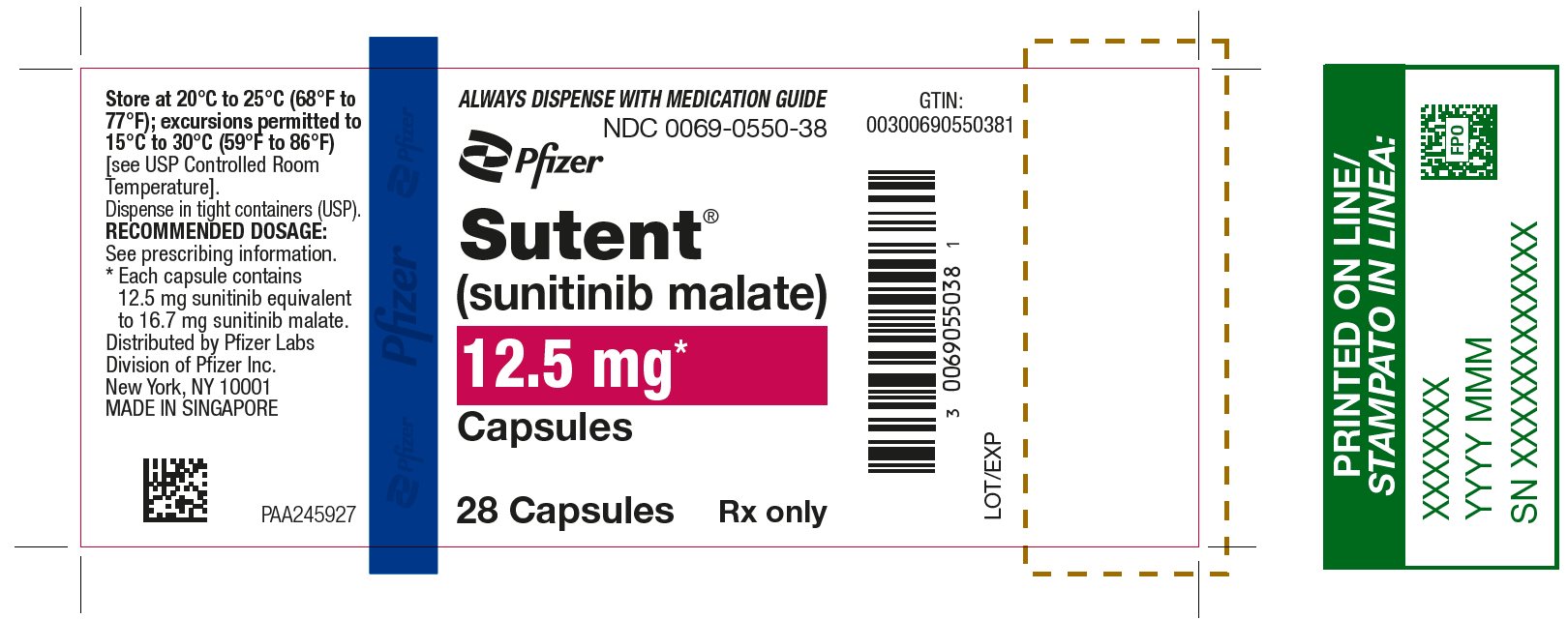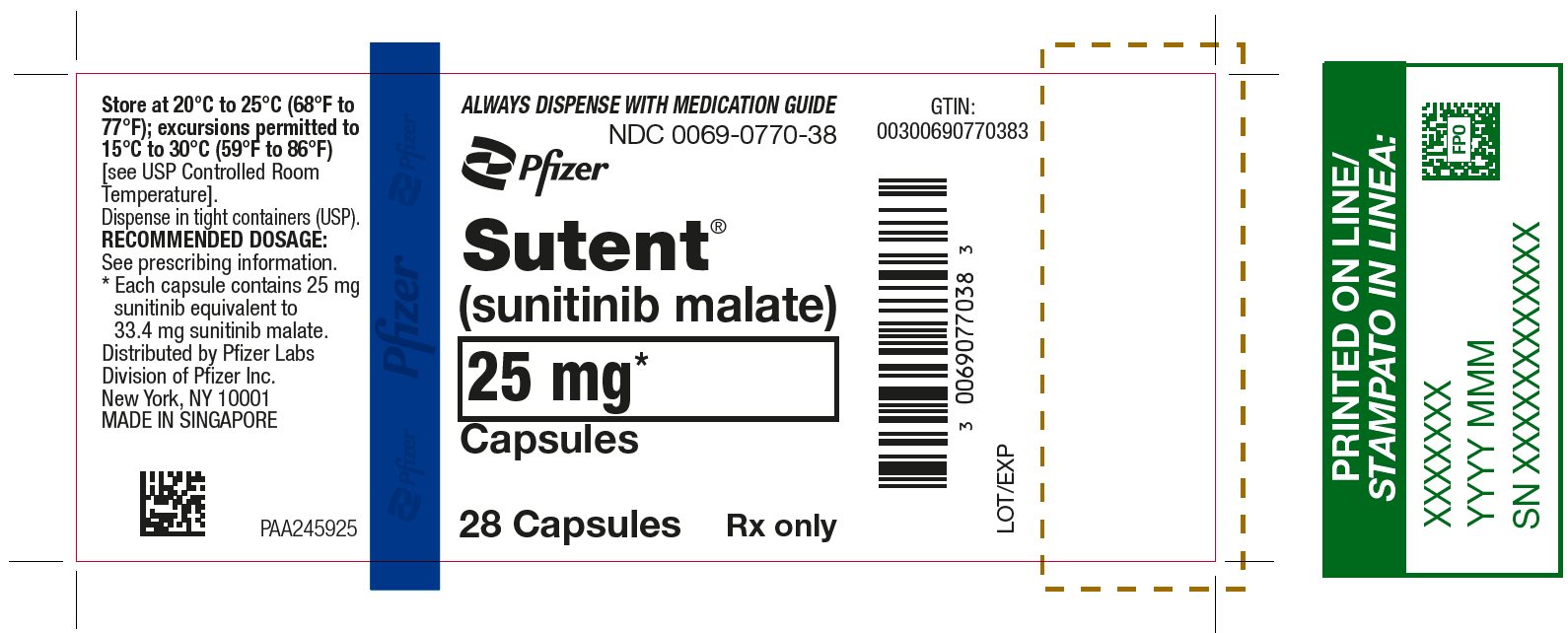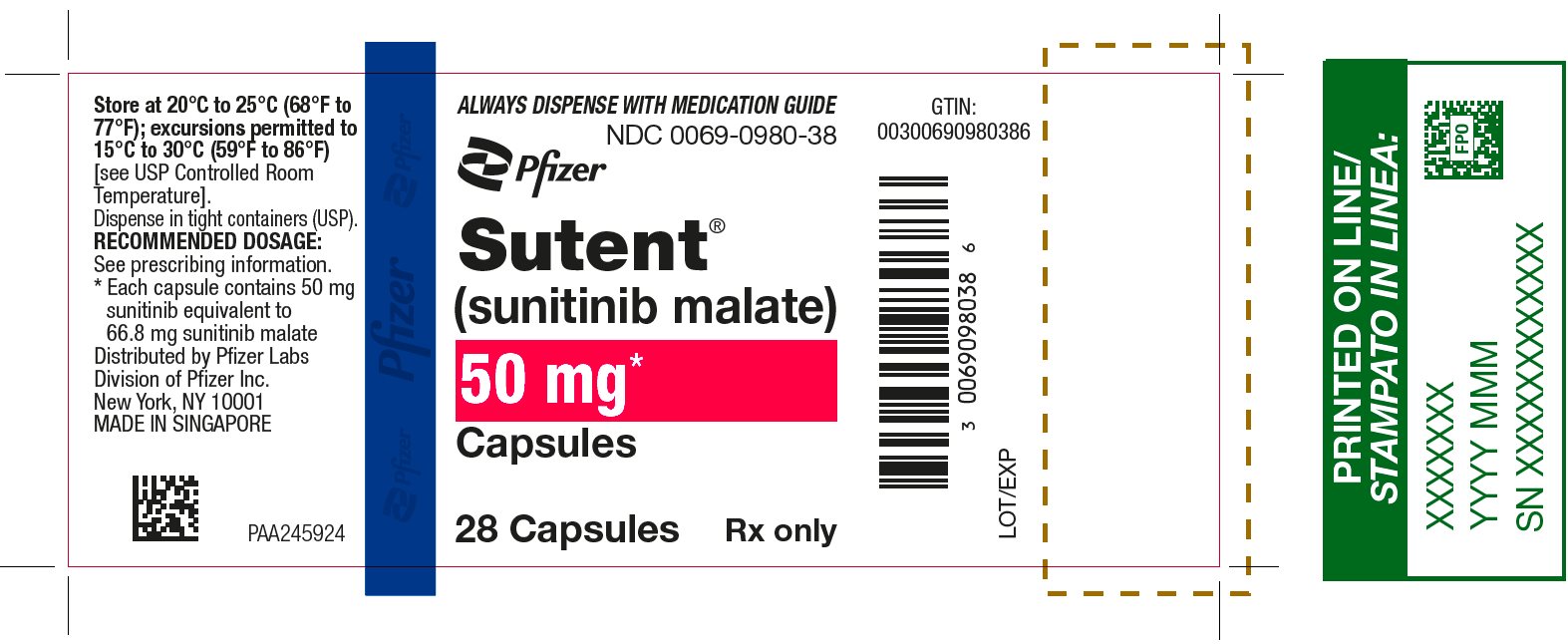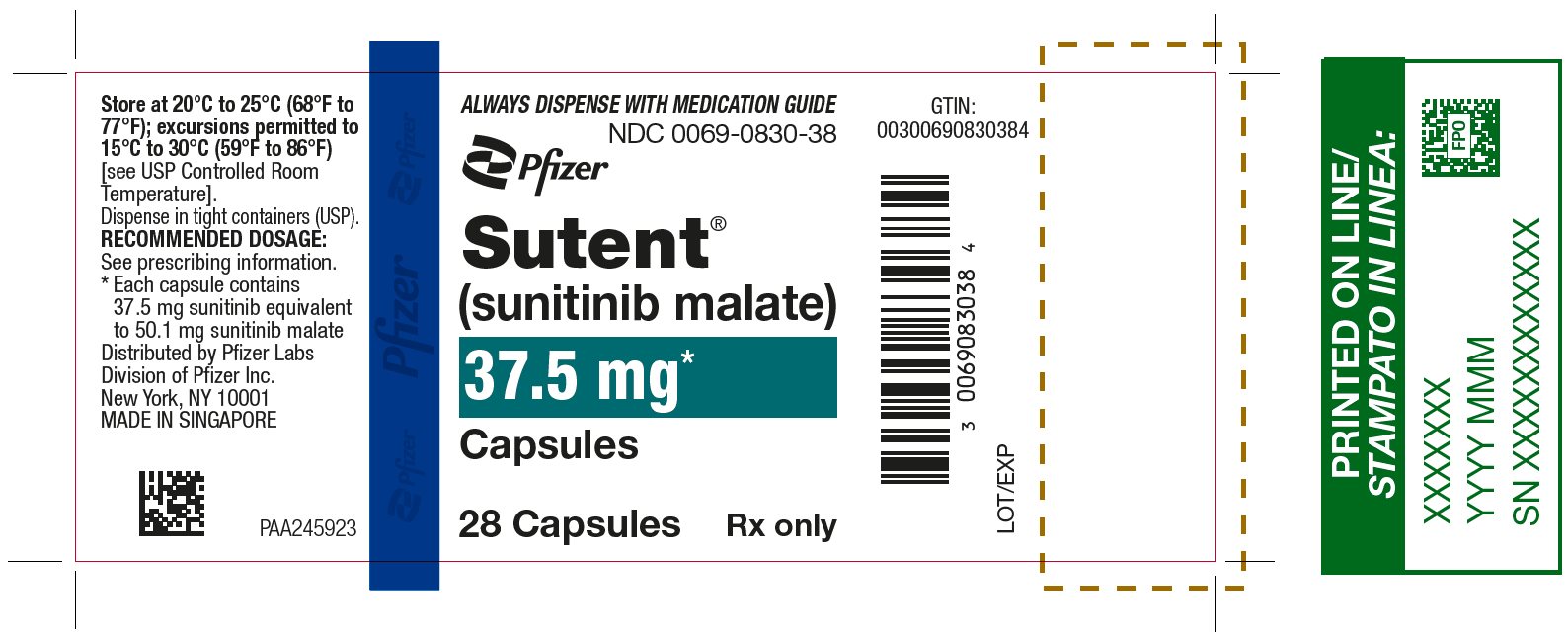 DRUG LABEL: SUTENT
NDC: 0069-0550 | Form: CAPSULE
Manufacturer: Pfizer Laboratories Div Pfizer Inc
Category: prescription | Type: HUMAN PRESCRIPTION DRUG LABEL
Date: 20260220

ACTIVE INGREDIENTS: SUNITINIB MALATE 12.5 mg/1 1
INACTIVE INGREDIENTS: MANNITOL; CROSCARMELLOSE SODIUM; POVIDONE K25; MAGNESIUM STEARATE; GELATIN, UNSPECIFIED; TITANIUM DIOXIDE; FERRIC OXIDE RED; SHELLAC; PROPYLENE GLYCOL; SODIUM HYDROXIDE; POVIDONE, UNSPECIFIED; POTASSIUM HYDROXIDE

HIGHLIGHTS OF PRESCRIBING INFORMATION

These highlights do not include all the information needed to use SUTENT safely and effectively. See full prescribing information for SUTENT.
SUTENT® (sunitinib malate) capsules, for oral use
Initial U.S. Approval: 2006

WARNING: HEPATOTOXICITY

See full prescribing information for complete boxed warning.

Hepatotoxicity may be severe, and in some cases fatal. Monitor hepatic function and interrupt, dose reduce, or discontinue SUTENT as recommended [see Warnings and Precautions (5.1)].

1 INDICATIONS AND USAGE

SUTENT is a kinase inhibitor indicated for:

- treatment of adult patients with gastrointestinal stromal tumor (GIST) after disease progression on or intolerance to imatinib mesylate. (1.1)
- treatment of adult patients with advanced renal cell carcinoma (RCC). (1.2)
- adjuvant treatment of adult patients at high risk of recurrent RCC following nephrectomy. (1.3)
- treatment of progressive, well-differentiated pancreatic neuroendocrine tumors (pNET) in adult patients with unresectable locally advanced or metastatic disease. (1.4)

2 DOSAGE AND ADMINISTRATION

GIST and Advanced RCC:

- The recommended dosage is 50 mg orally once daily for the first 4 weeks of each 6-week cycle (Schedule 4/2). (2.1)

Adjuvant Treatment of RCC:

- The recommended dosage is 50 mg orally once daily for the first 4 weeks of a 6-week cycle (Schedule 4/2) for a maximum of 9 cycles. (2.2)

pNET:

- The recommended dosage is 37.5 mg orally once daily. (2.3)

3 DOSAGE FORMS AND STRENGTHS

Capsules: 12.5 mg, 25 mg, 37.5 mg, 50 mg sunitinib (3)

4 CONTRAINDICATIONS

None (4)

5 WARNINGS AND PRECAUTIONS

- Hepatotoxicity: Fatal liver failure has been observed. Monitor liver function tests at baseline, during each cycle, and as clinically indicated. Interrupt SUTENT for Grade 3 hepatotoxicity until resolution to Grade ≤1 or baseline and resume SUTENT at a reduced dose; discontinue if no resolution. Discontinue SUTENT in patients with Grade 4 hepatoxicity, in patients who have subsequent severe changes in liver function tests or other signs and symptoms of liver failure. (2.4, 5.1)
- Cardiovascular Events: Myocardial ischemia, myocardial infarction, heart failure, cardiomyopathy, and decreased left ventricular ejection fraction (LVEF) to below the lower limit of normal including death have occurred. Monitor for signs and symptoms of congestive heart failure and consider monitoring LVEF at baseline and periodically during treatment. Discontinue SUTENT for clinical manifestations of congestive heart failure. Interrupt and/or dose reduce for decreased LVEF. (5.2)
- QT Interval Prolongation and Torsade de Pointes: Monitor patients at higher risk for developing QT interval prolongation. Consider monitoring of electrocardiograms and electrolytes. (5.3)
- Hypertension: Monitor blood pressure at baseline and as clinically indicated. Initiate and/or adjust antihypertensive therapy as appropriate. Interrupt SUTENT for Grade 3 hypertension until resolution to Grade ≤1 or baseline, then resume SUTENT at a reduced dose. Discontinue SUTENT in patients who develop Grade 4 hypertension. (5.4)
- Hemorrhagic Events: Tumor-related hemorrhage and viscus perforation (both with fatal events) have occurred. Perform serial complete blood counts and physical examinations. Interrupt SUTENT for Grade 3 or 4 hemorrhagic events until resolution to Grade ≤1 or baseline, then resume at a reduced dose; discontinue if no resolution. (5.5)
- Tumor Lysis Syndrome (TLS): TLS (some fatal) has been reported primarily in patients with RCC and GIST. Monitor these patients and treat as clinically indicated. (5.6)
- Thrombotic microangiopathy (TMA): TMA, including thrombotic thrombocytopenic purpura and hemolytic uremic syndrome, sometimes leading to renal failure or a fatal outcome, has been reported. Discontinue SUTENT for TMA. (5.7)
- Proteinuria: Renal failure or a fatal outcome has occurred. Monitor urine protein. Interrupt treatment for 24-hour urine protein of 3 or more grams. Discontinue for repeat episodes of 24-hour urine protein of 3 or more grams despite dose reductions or nephrotic syndrome. (5.8)
- Dermatologic Toxicities: Necrotizing fasciitis, erythema multiforme, Stevens-Johnson syndrome (SJS), and toxic epidermal necrolysis (TEN) (some fatal) have occurred. Discontinue SUTENT for these events. (5.9)
- Reversible Posterior Leukoencephalopathy Syndrome (RPLS): RPLS (some fatal) has been reported. Monitor for signs and symptoms of RPLS. Withhold SUTENT until resolution. (5.10)
- Thyroid Dysfunction: Monitor thyroid function at baseline, periodically during treatment, and as clinically indicated. Initiate and/or adjust therapy for thyroid dysfunction as appropriate. (5.11)
- Hypoglycemia: Check blood glucose levels regularly and assess if antidiabetic drug dose modifications are required. (5.12)
- Osteonecrosis of the Jaw (ONJ): Withhold SUTENT for at least 3 weeks prior to invasive dental procedure and for development of ONJ until complete resolution. (5.13)
- Impaired Wound Healing: Withhold SUTENT for at least 3 weeks prior to elective surgery. Do not administer for at least 2 weeks following major surgery and until adequate wound healing. The safety of resumption of SUTENT after resolution of wound healing complications has not been established. (5.14)
- Embryo-Fetal Toxicity: Can cause fetal harm. Advise patients of potential risk to a fetus and to use effective contraception. (5.15, 8.1, 8.3)

6 ADVERSE REACTIONS

- The most common adverse reactions (≥25%) are fatigue/asthenia, diarrhea, mucositis/stomatitis, nausea, decreased appetite/anorexia, vomiting, abdominal pain, hand-foot syndrome, hypertension, bleeding events, dysgeusia/altered taste, dyspepsia, and thrombocytopenia. (6)

To report SUSPECTED ADVERSE REACTIONS, contact Pfizer Inc. at 1-800-438-1985 or FDA at 1-800-FDA-1088 or www.fda.gov/medwatch.

7 DRUG INTERACTIONS

- CYP3A4 Inhibitors: Consider dose reduction of SUTENT when administered with strong CYP3A4 inhibitors. (7.1)
- CYP3A4 Inducers: Consider dose increase of SUTENT when administered with strong CYP3A4 inducers. (7.1)

8 USE IN SPECIFIC POPULATIONS

- Lactation: Advise not to breastfeed. (8.2)

FULL PRESCRIBING INFORMATION

WARNING: HEPATOTOXICITY

Hepatotoxicity may be severe, and in some cases, fatal. Monitor hepatic function and interrupt, dose reduce, or discontinue SUTENT as recommended [see Warnings and Precautions (5.1)].

1 INDICATIONS AND USAGE

1.1 Gastrointestinal Stromal Tumor

SUTENT is indicated for the treatment of adult patients with gastrointestinal stromal tumor (GIST) after disease progression on or intolerance to imatinib mesylate.

1.2 Advanced Renal Cell Carcinoma

SUTENT is indicated for the treatment of adult patients with advanced renal cell carcinoma (RCC).

1.3 Adjuvant Treatment of Renal Cell Carcinoma

SUTENT is indicated for the adjuvant treatment of adult patients at high risk of recurrent RCC following nephrectomy.

1.4 Advanced Pancreatic Neuroendocrine Tumors

SUTENT is indicated for the treatment of progressive, well-differentiated pancreatic neuroendocrine tumors (pNET) in adult patients with unresectable locally advanced or metastatic disease.

2 DOSAGE AND ADMINISTRATION

2.1 Recommended Dosage for GIST and Advanced RCC

The recommended dosage of SUTENT for gastrointestinal stromal tumor (GIST) and advanced renal cell carcinoma (RCC) is 50 mg taken orally once daily, on a schedule of 4 weeks on treatment followed by 2 weeks off (Schedule 4/2) until disease progression or unacceptable toxicity. SUTENT may be taken with or without food.

2.2 Recommended Dosage for Adjuvant Treatment of RCC

The recommended dosage of SUTENT for the adjuvant treatment of RCC is 50 mg taken orally once daily, on a schedule of 4 weeks on treatment followed by 2 weeks off (Schedule 4/2), for nine 6-week cycles. SUTENT may be taken with or without food.

2.3 Recommended Dosage for pNET

The recommended dosage of SUTENT for pancreatic neuroendocrine tumors (pNET) is 37.5 mg taken orally once daily until disease progression or unacceptable toxicity. SUTENT may be taken with or without food.

2.4 Dosage Modifications for Adverse Reactions

To manage adverse reactions, the recommended dosage modifications are provided in Table 1. Table 2 provides the recommended dosage reductions of SUTENT for adverse reactions.

Table 1. Recommended Dosage Reductions of SUTENT for Adverse Reactions
Indications | GIST | RCC |  | pNET
Indications | GIST | Advanced RCC | Adjuvant RCC | pNET
First dose reduction | 37.5 mg once daily | 37.5 mg once daily | 37.5 mg once daily | 25 mg once daily
Second dose reduction | 25 mg once daily | 25 mg once daily | NA | NA

Table 2. Recommended Dosage Modifications for SUTENT for Adverse Reactions
Adverse Reaction | Severity | Dosage Modifications for SUTENT
Hepatotoxicity [see Warnings and Precautions (5.1)] | Grade 3 | - Withhold until resolution to Grade 0 to 1 or baseline. - Resume at a reduced dose. - For recurring Grade 3 permanently discontinue.
Hepatotoxicity [see Warnings and Precautions (5.1)] | Grade 4 | - Permanently discontinue.
Cardiovascular events [see Warnings and Precautions (5.2)] | Asymptomatic cardiomyopathy (left ventricular ejection fraction greater than 20% but less than 50% below baseline or below the lower limit of normal if baseline was not obtained) | - Withhold until resolution to Grade 0 to 1 or baseline. - Resume at reduced dose.
Cardiovascular events [see Warnings and Precautions (5.2)] | Clinically manifested congestive heart failure (CHF) | - Permanently discontinue.
Hypertension [see Warnings and Precautions (5.4)] | Grade 3 | - Withhold until resolution to Grade 0 to 1 or baseline. - Resume at a reduced dose.
Hypertension [see Warnings and Precautions (5.4)] | Grade 4 | - Permanently discontinue.
Hemorrhagic events [see Warnings and Precautions (5.5)] | Grade 3 or 4 | - Withhold until resolution to Grade 0 to 1 or baseline. - Either resume at a reduced dose or discontinue depending on the severity and persistence of adverse reaction.
Thrombotic microangiopathy [see Warnings and Precautions (5.7)] | Any Grade | - Permanently discontinue.
Proteinuria or Nephrotic syndrome [see Warnings and Precautions (5.8)] | 3 or more grams proteinuria in 24 hours in the absence of nephrotic syndrome | - Withhold until resolution to Grade 0 to 1 or baseline. - Resume at a reduced dose.
Proteinuria or Nephrotic syndrome [see Warnings and Precautions (5.8)] | Nephrotic syndrome or recurrent proteinuria of 3 or more grams per 24 hours despite dose reductions | - Permanently discontinue.
Dermatological toxicities Erythema multiforme (EM), Stevens-Johnson syndrome (SJS), toxic epidermal necrolysis (TEN), Necrotizing fasciitis [see Warnings and Precautions (5.9)] | Any Grade | - Permanently discontinue.
Reversible posterior leukoencephalopathy syndrome [see Warnings and Precautions (5.10)] | Any Grade | - Permanently discontinue.
Osteonecrosis of the jaw [see Warnings and Precautions (5.13)] | Any Grade | - The safety of resumption of SUTENT after osteonecrosis has not been established. - Either resume at a reduced dose or discontinue depending on the severity and persistence of the adverse reaction.
Impaired wound healing [see Warnings and Precautions (5.14)] | Any Grade | - The safety of resumption of SUTENT after resolution of wound healing has not been established. - Either resume at a reduced dose or discontinue depending on the severity and persistence of the adverse reaction.

2.5 Dosage Modification for Drug Interactions

Strong CYP3A4 Inhibitors

Select an alternate concomitant medication with no or minimal enzyme inhibition potential. If coadministration of SUTENT with a strong CYP3A4 inhibitor cannot be avoided, consider a dose reduction for SUTENT to a minimum dosage as follows [see Drug Interactions (7.1)]:

- GIST and RCC: 37.5 mg orally once daily, on a schedule of 4 weeks on treatment followed by 2 weeks off (Schedule 4/2)
- pNET: 25 mg orally once daily

Strong CYP3A4 Inducers

Select an alternate concomitant medication with no or minimal enzyme induction potential. If coadministration of SUTENT with a strong CYP3A4 inducer cannot be avoided, consider a dose increase for SUTENT to a maximum dosage as follows:

- GIST and RCC: 87.5 mg orally once daily, on a schedule of 4 weeks on treatment followed by 2 weeks off (Schedule 4/2)
- pNET: 62.5 mg orally once daily

If the dose of SUTENT is increased, monitor patients carefully for adverse reactions [see Drug Interactions (7.1)].

2.6 Dosage Modification for End-Stage Renal Disease Patients on Hemodialysis

No starting dose adjustment is required in patients with end-stage renal disease (ESRD) on hemodialysis. However, given the decreased exposure compared to patients with normal renal function, subsequent doses may be increased gradually up to 2-fold based on safety and tolerability [see Clinical Pharmacology (12.3)].

3 DOSAGE FORMS AND STRENGTHS

Capsules, hard gelatin:

- 12.5 mg sunitinib: orange cap and orange body, printed with white ink “Pfizer” on the cap and “STN 12.5 mg” on the body.
- 25 mg sunitinib: caramel cap and orange body, printed with white ink “Pfizer” on the cap and “STN 25 mg” on the body.
- 37.5 mg sunitinib: yellow cap and yellow body, printed with black ink “Pfizer” on the cap and “STN 37.5 mg” on the body.
- 50 mg sunitinib: caramel top and caramel body, printed with white ink “Pfizer” on the cap and “STN 50 mg” on the body.

4 CONTRAINDICATIONS

None.

5 WARNINGS AND PRECAUTIONS

5.1 Hepatotoxicity

SUTENT can cause severe hepatotoxicity, resulting in liver failure or death. In the pooled safety population, liver failure occurred in <1% of patients in clinical trials. Liver failure include jaundiced, elevated transaminases and/or hyperbilirubinemia in conjunction with encephalopathy, coagulopathy, and/or renal failure.

Monitor liver function tests (alanine aminotransferase [ALT], aspartate aminotransferase [AST], and bilirubin) at baseline, during each cycle, and as clinically indicated. Interrupt SUTENT for Grade 3 hepatotoxicity until resolution to Grade ≤1 or baseline, then resume SUTENT at a reduced dose.

Discontinue SUTENT in patients with Grade 4 hepatotoxicity, in patients without resolution of Grade 3 hepatotoxicity, in patients who subsequently experience severe changes in liver function tests and in patients who have other signs and symptoms of liver failure. Safety in patients with ALT or AST >2.5 × upper limit of normal (ULN) or with >5 × ULN and liver metastases has not been established.

5.2 Cardiovascular Events

Cardiovascular events, including heart failure, cardiomyopathy, myocardial ischemia, and myocardial infarction, some of which were fatal, have been reported.

In pooled safety population, 3% of patients experienced heart failure; 71% of the patients with heart failure were reported as recovered. Fatal cardiac failure was reported in <1% of patients.

In the adjuvant treatment of RCC study, 11 patients experienced Grade 2 decreased ejection fraction (left ventricular ejection fraction [LVEF] 40% to 50% and a 10% to 19% decrease from baseline). In 3 of these 11 patients, the ejection fractions arm did not return to ≥50% or baseline by the time of last measurement. No patients who received SUTENT were diagnosed with CHF.

Patients who presented with cardiac events within 12 months prior to SUTENT administration, such as myocardial infarction (including severe/unstable angina), coronary/peripheral artery bypass graft, symptomatic CHF, cerebrovascular accident or transient ischemic attack, or pulmonary embolism were excluded from SUTENT clinical studies. Patients with prior anthracycline use or cardiac radiation were also excluded from some studies. It is unknown whether patients with these concomitant conditions may be at a higher risk of developing left ventricular dysfunction.

Consider monitoring LVEF at baseline and periodically as clinically indicated. Carefully monitor patients for clinical signs and symptoms of congestive heart failure (CHF). Discontinue SUTENT in patients who experience clinical manifestations of CHF. Interrupt SUTENT and/or reduce the dose in patients without clinical evidence of CHF who have an ejection fraction of greater than 20% but less than 50% below baseline or below the lower limit of normal if baseline ejection fraction was not obtained.

5.3 QT Interval Prolongation and Torsade de Pointes

SUTENT can cause QT interval prolongation in a dose-dependent manner, which may lead to an increased risk for ventricular arrhythmias including Torsade de Pointes. Torsade de Pointes was observed in <0.1% of patients.

Monitor patients who are at higher risk of developing QT interval prolongation, including patients with a history of QT interval prolongation, patients who are taking antiarrhythmics, or patients with relevant pre-existing cardiac disease, bradycardia, or electrolyte disturbances. Consider periodic monitoring of electrocardiograms and electrolytes (i.e., magnesium, potassium) during treatment with SUTENT.

Monitor QT interval more frequently when SUTENT is concomitantly administered with strong CYP3A4 inhibitors or drugs known to prolong QT interval. Consider dose reducing SUTENT [see Dosage and Administration (2.5), Drug Interactions (7.2)].

5.4 Hypertension

In the pooled safety population, 29% of patients experienced hypertension. Grade 3 hypertension was reported in 7% of patients, and Grade 4 hypertension was reported in 0.2%.

Monitor blood pressure at baseline and as clinically indicated. Initiate and/or adjust antihypertensive therapy as appropriate. In cases of Grade 3 hypertension, withhold SUTENT until resolution to Grade ≤1 or baseline, then resume SUTENT at a reduced dose. Discontinue SUTENT in patients with who develop Grade 4 hypertension.

5.5 Hemorrhagic Events and Viscus Perforation

Hemorrhagic events, some of which were fatal, have involved the gastrointestinal tract, respiratory tract, tumor, urinary tract, and brain. In the pooled safety population, 30% of patients experienced hemorrhagic events, including Grade 3 or 4 in 4.2% of patients. Epistaxis was the most common hemorrhagic event and gastrointestinal hemorrhage was the most common Grade 3–5 event.

Tumor-related hemorrhage was observed in patients treated with SUTENT. These events may occur suddenly, and in the case of pulmonary tumors, may present as severe and life-threatening hemoptysis or pulmonary hemorrhage. Pulmonary hemorrhage, some with a fatal outcome, was observed in patients treated with SUTENT for metastatic RCC, GIST, and metastatic lung cancer. SUTENT is not approved for use in patients with lung cancer.

Serious, sometimes fatal, gastrointestinal complications including gastrointestinal perforation, have been reported in patients with intra-abdominal malignancies treated with SUTENT.

Include serial complete blood counts (CBCs) and physical examinations with the clinical assessment of hemorrhagic events. Interrupt SUTENT for Grade 3 or 4 hemorrhagic events until resolution to Grade ≤1 or baseline, then resume SUTENT at a reduced dose.

Discontinue SUTENT in patients without resolution of Grade 3 or 4 hemorrhagic events.

5.6 Tumor Lysis Syndrome (TLS)

Tumor Lysis Syndrome (TLS), some fatal, occurred in clinical trials and has been reported in postmarketing experience, primarily in patients with RCC or GIST. Patients generally at risk of TLS are those with high tumor burden prior to treatment. Monitor these patients for TLS and manage as appropriate.

5.7 Thrombotic Microangiopathy (TMA)

Thrombotic Microangiopathy (TMA), including thrombotic thrombocytopenic purpura and hemolytic uremic syndrome, sometimes leading to renal failure or a fatal outcome, occurred in clinical trials and in postmarketing experience of SUTENT as monotherapy and administered in combination with bevacizumab. SUTENT is not approved for use in combination with bevacizumab.

Discontinue SUTENT in patients developing TMA. Reversal of the effects of TMA has been observed after SUTENT was discontinued.

5.8 Proteinuria

Proteinuria and nephrotic syndrome have been reported. Some of these cases have resulted in renal failure and fatal outcomes.

Monitor patients for the development or worsening of proteinuria. Perform baseline and periodic urinalyses during treatment, with follow up measurement of 24-hour urine protein as clinically indicated. Interrupt SUTENT and dose reduce for 24-hour urine protein of 3 or more grams. Discontinue SUTENT for patients with nephrotic syndrome or repeat episodes of 24-hour urine protein of 3 or more grams despite dose reductions. The safety of continued SUTENT treatment in patients with moderate to severe proteinuria has not been evaluated.

5.9 Dermatologic Toxicities

Severe cutaneous adverse reactions have been reported, including erythema multiforme (EM), Stevens-Johnson syndrome (SJS), and toxic epidermal necrolysis (TEN), some of which were fatal. Permanently discontinue SUTENT for these severe cutaneous adverse reactions.

Necrotizing fasciitis, including fatal cases, has been reported in patients treated with SUTENT, including of the perineum and secondary to fistula formation. Discontinue SUTENT in patients who develop necrotizing fasciitis.

5.10 Reversible Posterior Leukoencephalopathy Syndrome (RPLS)

Reversible posterior leukoencephalopathy syndrome (RPLS) has been reported in <1% of patients, some of which were fatal. Patients can present with hypertension, headache, decreased alertness, altered mental functioning, and visual loss, including cortical blindness. Magnetic resonance imaging is necessary to confirm the diagnosis. Discontinue SUTENT in patients developing RPLS.

5.11 Thyroid Dysfunction

Hyperthyroidism, some followed by hypothyroidism, have been reported in clinical trials and through postmarketing experience of SUTENT.

Monitor thyroid function at baseline, periodically during treatment and as clinically indicated. Monitor patients closely for signs and symptoms of thyroid dysfunction, including hypothyroidism, hyperthyroidism, and thyroiditis, during treatment with SUTENT. Initiate and/or adjust therapies for thyroid dysfunction as appropriate.

5.12 Hypoglycemia

SUTENT can result in symptomatic hypoglycemia, which may lead to loss of consciousness, or require hospitalization. In the pooled safety population, hypoglycemia occurred in 2% of the patients treated with SUTENT. Hypoglycemia has occurred in clinical trials in 2% of the patients treated with SUTENT for advanced RCC (Study 3) and GIST (Study 1) (n=577) and in approximately 10% of the patients treated with SUTENT for pNET (Study 6) (n=83). For patients being treated with SUTENT for pNET, pre-existing abnormalities in glucose homeostasis were not present in all patients who experienced hypoglycemia. Reductions in blood glucose levels may be worse in patients with diabetes.

Check blood glucose levels at baseline, regularly during treatment, as clinically indicated and after discontinuation of SUTENT. In patients with diabetes, assess if antidiabetic therapies need to be adjusted to minimize the risk of hypoglycemia.

5.13 Osteonecrosis of the Jaw (ONJ)

Osteonecrosis of the Jaw (ONJ) occurred in patients treated with SUTENT. Concomitant exposure to other risk factors, such as bisphosphonates or dental disease/invasive dental procedures, may increase the risk of ONJ. Perform an oral examination prior to initiation of SUTENT and periodically during SUTENT therapy. Advise patients regarding good oral hygiene practices. Withhold SUTENT treatment for at least 3 weeks prior to scheduled dental surgery or invasive dental procedures, if possible. Withhold SUTENT for development of ONJ until complete resolution. The safety of resumption of SUTENT after resolution of osteonecrosis of the jaw has not been established.

5.14 Impaired Wound Healing

Impaired wound healing has been reported in patients who received SUTENT [see Adverse Reactions (6.2)].

Withhold SUTENT for at least 3 weeks prior to elective surgery. Do not administer for at least 2 weeks following major surgery and until adequate wound healing. The safety of resumption of SUTENT after resolution of wound healing complications has not been established.

5.15 Embryo-Fetal Toxicity

Based on findings from animal studies and its mechanism of action, SUTENT can cause fetal harm when administered to pregnant woman. Administration of sunitinib to pregnant rats and rabbits during the period of organogenesis resulted in teratogenicity at approximately 5.5 and 0.3 times the combined systemic exposure [combined area under the curve (AUC) of sunitinib plus its active metabolite] in patients administered the recommended daily dose (RDD) of 50 mg, respectively.

Advise pregnant women of the potential risk to a fetus. Advise females of reproductive potential to use effective contraception during treatment with SUTENT and for 4 weeks following the final dose [see Use in Specific Populations (8.1, 8.3)].

6 ADVERSE REACTIONS

The following clinically significant adverse reactions are described elsewhere in the labeling.

- Hepatotoxicity [see Warnings and Precautions (5.1)]
- Cardiovascular Events [see Warnings and Precautions (5.2)]
- QT Interval Prolongation and Torsade de Pointes [see Warnings and Precautions (5.3)]
- Hypertension [see Warnings and Precautions (5.4)]
- Hemorrhagic Events [see Warnings and Precautions (5.5)]
- Tumor Lysis Syndrome [see Warnings and Precautions (5.6)]
- Thrombotic Microangiopathy [see Warnings and Precautions (5.7)]
- Proteinuria [see Warnings and Precautions (5.8)]
- Dermatologic Toxicities [see Warnings and Precautions (5.9)]
- Reversible Posterior Leukoencephalopathy Syndrome [see Warnings and Precautions (5.10)]
- Thyroid Dysfunction [see Warnings and Precautions (5.11)]
- Hypoglycemia [see Warnings and Precautions (5.12)]
- Osteonecrosis of the Jaw [see Warnings and Precautions (5.13)]
- Impaired Wound Healing [see Warnings and Precautions (5.14)]

6.1 Clinical Trials Experience

Because clinical trials are conducted under widely varying conditions, adverse reaction rates observed in the clinical trials of a drug cannot be directly compared to rates in the clinical trials of another drug and may not reflect the rates observed in practice.

The pooled safety population described in the Warnings and Precautions reflect exposure to SUTENT in 7527 patients with GIST, RCC (advanced and adjuvant), or pNET. In this pooled safety population, the most common adverse reactions (≥25%) were fatigue/asthenia, diarrhea, mucositis/stomatitis, nausea, decreased appetite/anorexia, vomiting, abdominal pain, hand-foot syndrome, hypertension, bleeding events, dysgeusia/altered taste, dyspepsia, and thrombocytopenia.

Gastrointestinal Stromal Tumor

The safety of SUTENT was evaluated in Study 1, a randomized, double-blind, placebo-controlled trial in which previously treated patients with GIST received SUTENT 50 mg daily on Schedule 4/2 (n=202) or placebo (n=102). Median duration of blinded study treatment was 2 cycles for patients on SUTENT (mean: 3.0; range: 1–9) and 1 cycle (mean; 1.8; range: 1–6) for patients on placebo at the time of the interim analysis.

Permanent discontinuation due to an adverse reaction occurred in 7% of patients in the SUTENT arm. Dose reductions occurred in 11% and dose interruptions occurred in 29% of patients who received SUTENT.

Table 3 summarizes the adverse reactions for Study 1.

Table 3. Adverse Reactions Reported in ≥10% of GIST Patients Who Received SUTENT in the Double-Blind Treatment Phase and More Commonly Than in Patients Given Placebo [Common Terminology Criteria for Adverse Events (CTCAE), version 3.0.] in Study 1
Adverse Reaction | GIST
Adverse Reaction | SUTENT (N=202) |  | Placebo (N=102)
Adverse Reaction | All Grades % | Grade 3–4 % | All Grades % | Grade 3–4 %
Any Adverse Reaction | 94 | 56 | 97 | 51
Gastrointestinal
Diarrhea | 40 | 4 | 27 | 0
Mucositis/stomatitis | 29 | 1 | 18 | 2
Constipation | 20 | 0 | 14 | 2
Metabolism/Nutrition
Anorexia [Includes decreased appetite.] | 33 | 1 | 29 | 5
Asthenia | 22 | 5 | 11 | 3
Dermatology
Skin discoloration | 30 | 0 | 23 | 0
Rash | 14 | 1 | 9 | 0
Hand-foot syndrome | 14 | 4 | 10 | 3
Neurology
Altered taste | 21 | 0 | 12 | 0
Cardiac
Hypertension | 15 | 4 | 11 | 0
Musculoskeletal
Myalgia/limb pain | 14 | 1 | 9 | 1
Abbreviations: GIST=gastrointestinal stromal tumor; N=number of patients.

Other clinically relevant adverse reactions included oral pain other than mucositis/stomatitis in 6%; hair color changes in 7%; alopecia in 5% of patients who received SUTENT.

Table 4 summarizes the laboratory abnormalities in Study 1.

Table 4. Laboratory Abnormalities Reported in ≥10% of GIST Patients Who Received SUTENT or Placebo in the Double-Blind Treatment Phase [Common Terminology Criteria for Adverse Events (CTCAE), version 3.0.] in Study 1
Laboratory Abnormality | GIST
Laboratory Abnormality | SUTENT (N=202) |  | Placebo (N=102)
Laboratory Abnormality | All Grades % | Grade 3–4, [Grade 4 laboratory abnormalities in patients on SUTENT included alkaline phosphatase (1%), lipase (2%), creatinine (1%), potassium decreased (1%), neutrophils (2%), hemoglobin (2%), and platelets (1%).] % | All Grades % | Grade 3–4, [Grade 4 laboratory abnormalities in patients on placebo included amylase (1%), lipase (1%), and hemoglobin (2%).] %
Any Laboratory Abnormality |  | 34 |  | 22
Hematology
Neutrophils decreased | 53 | 10 | 4 | 0
Lymphocytes decreased | 38 | 0 | 16 | 0
Platelets decreased | 38 | 5 | 4 | 0
Hemoglobin decreased | 26 | 3 | 22 | 2
Gastrointestinal
AST/ALT increased | 39 | 2 | 23 | 1
Lipase increased | 25 | 10 | 17 | 7
Alkaline phosphatase increased | 24 | 4 | 21 | 4
Amylase increased | 17 | 5 | 12 | 3
Total bilirubin increased | 16 | 1 | 8 | 0
Indirect bilirubin increased | 10 | 0 | 4 | 0
Renal/Metabolic
Creatinine increased | 12 | 1 | 7 | 0
Potassium decreased | 12 | 1 | 4 | 0
Sodium increased | 10 | 0 | 4 | 1
Cardiac
Decreased LVEF | 11 | 1 | 3 | 0
Abbreviations: ALT=alanine aminotransferase; AST=aspartate aminotransferase; GIST=gastrointestinal stromal tumor; LVEF=left ventricular ejection fraction; N=number of patients.

After an interim analysis, the study was unblinded and patients on the placebo arm were given the opportunity to receive open-label SUTENT [see Clinical Studies (14.1)]. For 241 patients randomized to the SUTENT arm, including 139 who received SUTENT in both the double-blind and open-label phases, the median duration of SUTENT treatment was 6 cycles (mean: 8.5; range: 1–44). For the 255 patients who ultimately received open-label SUTENT treatment, median duration of treatment was 6 cycles (mean: 7.8; range: 1–37) from the time of the unblinding.

Permanent discontinuation due to an adverse reaction occurred in 20% of patients who received SUTENT. Dosage interruption occurred in 46% and dose reduction occurred in 28% of patients who received SUTENT.

The most common Grade 3 or 4 adverse reactions in patients who received SUTENT in the open-label phase were fatigue (10%), hypertension (8%), asthenia (5%), diarrhea (5%), hand-foot syndrome (5%), nausea (4%), abdominal pain (3%), anorexia (3%), mucositis (2%), vomiting (2%), and hypothyroidism (2%).

Advanced Renal Cell Carcinoma

The safety of SUTENT was evaluated in Study 3, a double-blind, active-controlled trial in which previously untreated patients with locally advanced or metastatic RCC received SUTENT 50 mg daily on Schedule 4/2 (n=375) or interferon alfa 9 million International Units (MIU) (n=360). The median duration of treatment was 11.1 months (range: 0.4 to 46.1) for SUTENT treatment and 4.1 months (range: 0.1 to 45.6) for interferon alfa treatment.

Permanent discontinuation due to an adverse reaction occurred in 20% of patients in the SUTENT arm. Dose interruptions occurred in 54% and dose reductions occurred in 52% of patients who received SUTENT.

Table 5 summarizes the adverse reactions for Study 3.

Table 5. Adverse Reactions Reported in ≥10% of Patients With RCC Who Received SUTENT or Interferon Alfa [Common Terminology Criteria for Adverse Events (CTCAE), version 3.0.] in Study 3
Adverse Reaction | Treatment-Naïve RCC
Adverse Reaction | SUTENT (N=375) |  | Interferon Alfa (N=360)
Adverse Reaction | All Grades % | Grade 3–4 [Grade 4 ARs in patients on SUTENT included back pain (1%), arthralgia (<1%), dyspnea (<1%), asthenia (<1%), fatigue (<1%), limb pain (<1%), and rash (<1%).] % | All Grades % | Grade 3–4 [Grade 4 ARs in patients on interferon alfa included dyspnea (1%), fatigue (1%), abdominal pain (<1%), and depression (<1%).] %
Any Adverse Reaction | 99 | 77 | 99 | 55
Gastrointestinal
Diarrhea | 66 | 10 | 21 | <1
Nausea | 58 | 6 | 41 | 2
Mucositis/stomatitis | 47 | 3 | 5 | <1
Vomiting | 39 | 5 | 17 | 1
Dyspepsia | 34 | 2 | 4 | 0
Abdominal pain [Includes flank pain.] | 30 | 5 | 12 | 1
Constipation | 23 | 1 | 14 | <1
Dry mouth | 13 | 0 | 7 | <1
Oral pain | 14 | <1 | 1 | 0
Flatulence | 14 | 0 | 2 | 0
GERD/reflux esophagitis | 12 | <1 | 1 | 0
Glossodynia | 11 | 0 | 1 | 0
Hemorrhoids | 10 | 0 | 2 | 0
Constitutional
Fatigue | 62 | 15 | 56 | 15
Asthenia | 26 | 11 | 22 | 6
Fever | 22 | 1 | 37 | <1
Weight decreased | 16 | <1 | 17 | 1
Chills | 14 | 1 | 31 | 0
Chest Pain | 13 | 2 | 7 | 1
Influenza like illness | 5 | 0 | 15 | <1
Metabolism/Nutrition
Anorexia [Includes decreased appetite.] | 48 | 3 | 42 | 2
Neurology
Altered taste [Includes ageusia, hypogeusia, and dysgeusia.] | 47 | <1 | 15 | 0
Headache | 23 | 1 | 19 | 0
Dizziness | 11 | <1 | 14 | 1
Hemorrhage/Bleeding
Bleeding, all sites | 37 | 4 [Includes 1 patient with Grade 5 gastric hemorrhage.] | 10 | 1
Cardiac
Hypertension | 34 | 13 | 4 | <1
Edema peripheral | 24 | 2 | 5 | 1
Ejection fraction decreased | 16 | 3 | 5 | 2
Dermatology
Rash | 29 | 2 | 11 | <1
Hand-foot syndrome | 29 | 8 | 1 | 0
Skin discoloration/yellow skin | 25 | <1 | 0 | 0
Dry skin | 23 | <1 | 7 | 0
Hair color changes | 20 | 0 | <1 | 0
Alopecia | 14 | 0 | 9 | 0
Erythema | 12 | <1 | 1 | 0
Pruritus | 12 | <1 | 7 | <1
Musculoskeletal
Pain in extremity/limb discomfort | 40 | 5 | 30 | 2
Arthralgia | 30 | 3 | 19 | 1
Back pain | 28 | 5 | 14 | 2
Respiratory
Cough | 27 | 1 | 14 | <1
Dyspnea | 26 | 6 | 20 | 4
Nasopharyngitis | 14 | 0 | 2 | 0
Oropharyngeal pain | 14 | <1 | 2 | 0
Upper respiratory tract infection | 11 | <1 | 2 | 0
Endocrine
Hypothyroidism | 16 | 2 | 1 | 0
Psychiatric
Insomnia | 15 | <1 | 10 | 0
Depression [Includes depressed mood.] | 11 | 0 | 14 | 1
Abbreviations: ARs=adverse reactions; N=number of patients; RCC=renal cell carcinoma.

Table 6 summarizes the laboratory abnormalities in Study 3.

Table 6. Laboratory Abnormalities Reported in ≥10% of RCC Patients Who Received SUTENT or Interferon Alfa in Study 3
Laboratory Abnormality | Treatment-Naïve RCC
Laboratory Abnormality | SUTENT (N=375) |  | Interferon Alfa (N=360)
Laboratory Abnormality | All Grades [Common Terminology Criteria for Adverse Events (CTCAE), version 3.0.] % | Grade 3–4, [Grade 4 laboratory abnormalities in patients on SUTENT included uric acid (14%), lipase (3%), neutrophils (2%), lymphocytes (2%), hemoglobin (2%), platelets (1%), amylase (1%), ALT (<1%), creatine kinase (<1%), creatinine (<1%), glucose increased (<1%), calcium decreased (<1%), phosphorous (<1%), potassium increased (<1%), and sodium decreased (<1%).] % | All Grades % | Grade 3–4, [Grade 4 laboratory abnormalities in patients on interferon alfa included uric acid (8%), lymphocytes (2%), lipase (1%), neutrophils (1%), amylase (<1%), calcium increased (<1%), glucose decreased (<1%), potassium increased (<1%), and hemoglobin (<1%).] %
Hematology
Hemoglobin decreased | 79 | 8 | 69 | 5
Neutrophils decreased | 77 | 17 | 49 | 9
Platelets decreased | 68 | 9 | 24 | 1
Lymphocytes decreased | 68 | 18 | 68 | 26
Renal/Metabolic
Creatinine increased | 70 | <1 | 51 | <1
Creatine kinase increased | 49 | 2 | 11 | 1
Uric acid increased | 46 | 14 | 33 | 8
Calcium decreased | 42 | 1 | 40 | 1
Phosphorus decreased | 31 | 6 | 24 | 6
Albumin decreased | 28 | 1 | 20 | 0
Glucose increased | 23 | 6 | 15 | 6
Sodium decreased | 20 | 8 | 15 | 4
Glucose decreased | 17 | 0 | 12 | <1
Potassium increased | 16 | 3 | 17 | 4
Calcium increased | 13 | <1 | 10 | 1
Potassium decreased | 13 | 1 | 2 | <1
Sodium increased | 13 | 0 | 10 | 0
Gastrointestinal
AST increased | 56 | 2 | 38 | 2
Lipase increased | 56 | 18 | 46 | 8
ALT increased | 51 | 3 | 40 | 2
Alkaline phosphatase increased | 46 | 2 | 37 | 2
Amylase increased | 35 | 6 | 32 | 3
Total bilirubin increased | 20 | 1 | 2 | 0
Indirect bilirubin increased | 13 | 1 | 1 | 0
Abbreviations: ALT=alanine aminotransferase; AST=aspartate aminotransferase; N=number of patients; RCC=renal cell carcinoma.

Long-Term Safety in RCC

The long-term safety of SUTENT in patients with metastatic RCC was analyzed across 9 completed clinical studies conducted in the first-line, bevacizumab-refractory, and cytokine-refractory treatment settings. The analysis included 5739 patients, of whom 807 (14%) were treated for at least 2 years and 365 (6%) for at least 3 years. Prolonged treatment with SUTENT did not appear to be associated with new types of adverse reactions. There appeared to be no increase in the yearly incidence of adverse reactions at later time points. Hypothyroidism increased during the second year of treatment with new cases reported up to year 4.

Adjuvant Treatment of RCC

The safety of SUTENT was evaluated in S-TRAC, a randomized, double-blind, placebo-controlled trial in which patients who had undergone nephrectomy for RCC received SUTENT 50 mg daily on Schedule 4/2 (n=306) or placebo (n=304). The median duration of treatment was 12.4 months (range: 0.13 to 14.9) for SUTENT and 12.4 months (range: 0.03 to 13.7) for placebo.

Permanent discontinuation due to an adverse reaction occurred in 28% of patients in the SUTENT arm. Adverse reactions leading to permanent discontinuation in >2% of patients include hand-foot syndrome and fatigue/asthenia. Dosing interruptions occurred in 54% and dose reductions occurred in 46% of patients who received SUTENT.

Table 7 summarizes the adverse reactions in S-TRAC.

Table 7. Adverse Reactions Reported in ≥10% of Patients With RCC Who Received SUTENT and More Commonly Than in Patients Given Placebo [Common Terminology Criteria for Adverse Events (CTCAE), version 3.0.] in S-TRAC
Adverse Reaction | Adjuvant Treatment of RCC
Adverse Reaction | SUTENT (N=306) |  | Placebo (N=304)
Adverse Reaction | All Grades % | Grade 3–4 % | All Grades % | Grade 3–4 %
Any Adverse Reaction | 99 | 60 | 88 | 15
Gastrointestinal
Mucositis/Stomatitis [Includes mucosal inflammation, stomatitis aphthous ulcer, mouth ulceration, tongue ulceration, oropharyngeal pain, and oral pain.] | 61 | 6 | 15 | 0
Diarrhea | 57 | 4 | 22 | <1
Nausea | 34 | 2 | 15 | 0
Dyspepsia | 27 | 1 | 7 | 0
Abdominal pain [Includes abdominal pain, abdominal pain lower, and abdominal pain upper.] | 25 | 2 | 9 | <1
Vomiting | 19 | 2 | 7 | 0
Constipation | 12 | 0 | 11 | 0
Constitutional
Fatigue/Asthenia | 57 | 8 | 34 | 2
Localized edema [Includes edema localized, face edema, eyelid edema, periorbital edema, swelling face, and eye edema.] | 18 | <1 | <1 | 0
Pyrexia | 12 | <1 | 6 | 0
Dermatology
Hand-foot syndrome | 50 | 16 | 10 | <1
Rash [Includes dermatitis, dermatitis psoriasiform, exfoliative rash, genital rash, rash, rash erythematous, rash follicular, rash generalized, rash macular, rash maculopapular, rash papular, and rash pruritic.] | 24 | 2 | 12 | 0
Hair color changes | 22 | 0 | 2 | 0
Skin discoloration/Yellow skin | 18 | 0 | 1 | 0
Dry skin | 14 | 0 | 6 | 0
Cardiac
Hypertension [Includes hypertension, blood pressure increased, blood pressure systolic increased, blood pressure diastolic increased, and hypertensive crisis.] | 39 | 8 | 14 | 1
Edema/Peripheral edema | 10 | <1 | 7 | 0
Neurology
Altered taste [Includes ageusia, hypogeusia, and dysgeusia.] | 38 | <1 | 6 | 0
Headache | 19 | <1 | 12 | 0
Endocrine
Hypothyroidism/TSH increased | 24 | <1 | 4 | 0
Hemorrhage/Bleeding
Bleeding events, all sites [Includes epistaxis, gingival bleeding, rectal hemorrhage, hemoptysis, anal hemorrhage, upper gastrointestinal hemorrhage, and hematuria.] | 24 | <1 | 5 | <1
Metabolism/Nutrition
Anorexia/Decreased appetite | 19 | <1 | 5 | 0
Musculoskeletal
Pain in extremity | 15 | <1 | 7 | 0
Arthralgia | 11 | <1 | 10 | 0
Abbreviations: ARs=adverse reactions; N=number of patients; RCC=renal cell carcinoma.

Grade 4 adverse reactions in patients on SUTENT included hand-foot syndrome (1%), fatigue (<1%), abdominal pain (< 1%), stomatitis (<1%), and pyrexia (< 1%).

Grade 3–4 laboratory abnormalities that occurred in ≥2% of patients receiving SUTENT include neutropenia (13%), thrombocytopenia (5%), leukopenia (3%), lymphopenia (3%), elevated alanine aminotransferase (2%), elevated aspartate aminotransferase (2%), hyperglycemia (2%), and hyperkalemia (2%).

Advanced Pancreatic Neuroendocrine Tumors

The safety of SUTENT was evaluated in Study 6, a randomized, double-blind, placebo-controlled trial in which patients with progressive pNET received SUTENT 37.5 mg once daily (n=83) or placebo (n=82). The median number of days on treatment was 139 days (range: 13–532 days) for patients on SUTENT and 113 days (range: 1–614 days) for patients on placebo. Nineteen patients (23%) on SUTENT and 4 patients (5%) on placebo were on study for >1 year.

Permanent discontinuation due to an adverse reaction occurred in 22% in the SUTENT arm. Dose interruptions occurred in 30% and dose reductions occurred in 31% of patients who received SUTENT.

Table 8 summarizes the adverse reactions in Study 6.

Table 8. Adverse Reactions Reported in ≥10% of Patients With pNET Who Received SUTENT and More Commonly Than in Patients Given Placebo [Common Terminology Criteria for Adverse Events (CTCAE), version 3.0.] in Study 6
Adverse Reaction | pNET
Adverse Reaction | SUTENT (N=83) |  | Placebo (N=82)
Adverse Reaction | All Grades % | Grade 3–4 [Grade 4 adverse reactions in patients on SUTENT included fatigue (1%).] % | All Grades % | Grade 3–4 %
Any Adverse Reaction | 99 | 54 | 95 | 50
Gastrointestinal
Diarrhea | 59 | 5 | 39 | 2
Stomatitis/oral syndromes [Includes aphthous stomatitis, gingival pain, gingivitis, glossitis, glossodynia, mouth ulceration, oral discomfort, oral pain, tongue ulceration, mucosal dryness, mucosal inflammation, and dry mouth.] | 48 | 6 | 18 | 0
Nausea | 45 | 1 | 29 | 1
Abdominal pain [Includes abdominal discomfort, abdominal pain, and abdominal pain upper.] | 39 | 5 | 34 | 10
Vomiting | 34 | 0 | 31 | 2
Dyspepsia | 15 | 0 | 6 | 0
Constitutional
Asthenia | 34 | 5 | 27 | 4
Fatigue | 33 | 5 | 27 | 9
Weight decreased | 16 | 1 | 11 | 0
Dermatology
Hair color changes | 29 | 1 | 1 | 0
Hand-foot syndrome | 23 | 6 | 2 | 0
Rash | 18 | 0 | 5 | 0
Dry skin | 15 | 0 | 11 | 0
Cardiac
Hypertension | 27 | 10 | 5 | 1
Hemorrhage/Bleeding
Bleeding events [Includes hematemesis, hematochezia, hematoma, hemoptysis, hemorrhage, melena, and metrorrhagia.] | 22 | 0 | 10 | 4
Epistaxis | 21 | 1 | 5 | 0
Neurology
Dysgeusia | 21 | 0 | 5 | 0
Headache | 18 | 0 | 13 | 1
Psychiatric
Insomnia | 18 | 0 | 12 | 0
Musculoskeletal
Arthralgia | 15 | 0 | 6 | 0
Abbreviations: N=number of patients; pNET=pancreatic neuroendocrine tumors.

Table 9 summarizes the laboratory abnormalities in Study 6.

Table 9. Laboratory Abnormalities Reported in ≥10% of Patients With pNET Who Received SUTENT in Study 6
 | pNET
Laboratory Abnormality | SUTENT |  | Placebo
 | All Grades [The denominator used to calculate the rate varied from 52 to 82 for SUTENT and 39 to 80 for Placebo based on the number of patients with a baseline value and at least one post-treatment value. Common Terminology Criteria for Adverse Events (CTCAE), version 3.0.] % | Grade 3–4, [Grade 4 laboratory abnormalities in patients on SUTENT included creatinine (4%), lipase (4%), glucose decreased (2%), glucose increased (2%), neutrophils (2%), ALT (1%), AST (1%), platelets (1%), potassium increased (1%), and total bilirubin (1%).] % | All Grades % | Grade 3–4, [Grade 4 laboratory abnormalities in patients on placebo included creatinine (3%), alkaline phosphatase (1%), glucose increased (1%), and lipase (1%).] %
Gastrointestinal
AST increased | 72 | 5 | 70 | 3
Alkaline phosphatase increased | 63 | 10 | 70 | 11
ALT increased | 61 | 4 | 55 | 3
Total bilirubin increased | 37 | 1 | 28 | 4
Amylase increased | 20 | 4 | 10 | 1
Lipase increased | 17 | 5 | 11 | 4
Hematology
Neutrophils decreased | 71 | 16 | 16 | 0
Hemoglobin decreased | 65 | 0 | 55 | 1
Platelets decreased | 60 | 5 | 15 | 0
Lymphocytes decreased | 56 | 7 | 35 | 4
Renal/Metabolic
Glucose increased | 71 | 12 | 78 | 18
Albumin decreased | 41 | 1 | 37 | 1
Phosphorus decreased | 36 | 7 | 22 | 5
Calcium decreased | 34 | 0 | 19 | 0
Sodium decreased | 29 | 2 | 34 | 3
Creatinine increased | 27 | 5 | 28 | 5
Glucose decreased | 22 | 2 | 15 | 4
Potassium decreased | 21 | 4 | 14 | 0
Magnesium decreased | 19 | 0 | 10 | 0
Potassium increased | 18 | 1 | 11 | 1
Abbreviations: ALT=alanine aminotransferase; AST=aspartate aminotransferase; N=number of patients; pNET=pancreatic neuroendocrine tumors.

Venous Thromboembolic Events

In pooled safety population, 3.5% of patients experienced a venous thromboembolic event, including Grade 3–4 in 2.2% of patients.

Pancreatic Function

Pancreatitis was observed in 1 patient (1%) in the pNET study, 5 patients (1%) in the treatment-naïve RCC study, and 1 patient (<1%) in the adjuvant treatment for RCC study on SUTENT.

6.2 Postmarketing Experience

The following adverse reactions have been identified during postapproval use of SUTENT. Because these reactions are reported voluntarily from a population of uncertain size, it is not always possible to reliably estimate their frequency or establish a causal relationship to drug exposure.

- Blood and lymphatic system disorders: hemorrhage associated with thrombocytopenia [including some fatalities] .
- Gastrointestinal disorders: esophagitis.
- Hepatobiliary disorders: cholecystitis, particularly acalculous cholecystitis.
- Immune system disorders: hypersensitivity reactions, including angioedema.
- Infections and infestations: serious infection (with or without neutropenia). The infections most commonly observed with SUTENT include respiratory, urinary tract, skin infections, and sepsis/septic shock.
- Musculoskeletal and connective tissue disorders: fistula formation, sometimes associated with tumor necrosis and/or regression; myopathy and/or rhabdomyolysis with or without acute renal failure.
- Renal and urinary disorders: renal impairment and/or failure.
- Respiratory disorders: pulmonary embolism, pleural effusion.
- Skin and subcutaneous tissue disorders: pyoderma gangrenosum, including positive de-challenges.
- Vascular disorders: arterial (including aortic) aneurysms, dissections, and rupture; arterial thromboembolic events. The most frequent events included cerebrovascular accident, transient ischemic attack, and cerebral infarction.
- General disorders and administration site conditions: impaired wound healing.

7 DRUG INTERACTIONS

7.1 Effect of Other Drugs on SUTENT

Strong CYP3A4 Inhibitors

Co-administration with strong CYP3A4 inhibitors may increase sunitinib plasma concentrations [see Clinical Pharmacology (12.3)]. Select an alternate concomitant medication with no or minimal enzyme inhibition potential. Consider a dose reduction for SUTENT when it is co-administered with strong CYP3A4 inhibitors [see Dosage and Administration (2.5)].

Strong CYP3A4 Inducers

Co-administration with strong CYP3A4 inducers may decrease sunitinib plasma concentrations [see Clinical Pharmacology (12.3)]. Select an alternate concomitant medication with no or minimal enzyme induction potential. Consider a dose increase for SUTENT when it must be co-administered with CYP3A4 inducers [see Dosage and Administration (2.5)].

7.2 Drugs that Prolong QT Interval

SUTENT is associated with QTc interval prolongation [see Warnings and Precautions (5.3), Clinical Pharmacology (12.2)]. Monitor the QT interval with ECGs more frequently in patients who require treatment with concomitant medications known to prolong the QT interval.

8 USE IN SPECIFIC POPULATIONS

8.1 Pregnancy

Risk Summary

Based on animal reproduction studies and its mechanism of action, SUTENT can cause fetal harm when administered to a pregnant woman [see Clinical Pharmacology (12.1)]. There are no available data in pregnant women to inform a drug-associated risk. In animal developmental and reproductive toxicology studies, oral administration of sunitinib to pregnant rats and rabbits throughout organogenesis resulted in teratogenicity (embryolethality, craniofacial and skeletal malformations) at 5.5 and 0.3 times the combined AUC (the combined systemic exposure of sunitinib plus its active metabolite) in patients administered the recommended daily doses (RDD) of 50 mg, respectively (see Data). Advise females of reproductive potential of the potential risk to a fetus.

The estimated background risk of major birth defects and miscarriage for the indicated populations are unknown. All pregnancies have a background risk of birth defect, loss, or other adverse outcomes. In the U.S. general population, the estimated background risk of major birth defects and miscarriages in clinically recognized pregnancies is 2 to 4% and 15 to 20%, respectively.

Data

Animal Data

In a female fertility and early embryonic development study, female rats were administered oral sunitinib (0.5, 1.5, 5 mg/kg/day) for 21 days prior to mating and for 7 days after mating. Embryolethality was observed at 5 mg/kg/day (approximately 5 times the combined AUC in patients administered the RDD of 50 mg).

In embryo-fetal developmental toxicity studies, oral sunitinib was administered to pregnant rats (0.3, 1.5, 3, 5 mg/kg/day) and rabbits (0.5, 1, 5, 20 mg/kg/day) during the period of organogenesis. In rats, embryolethality and skeletal malformations of the ribs and vertebrae were observed at the dose of 5 mg/kg/day (approximately 5.5 times the combined AUC in patients administered the RDD of 50 mg). No adverse fetal effects were observed in rats at doses ≤3 mg/kg/day (approximately 2 times the combined AUC in patients administered the RDD of 50 mg). In rabbits, embryolethality was observed at 5 mg/kg/day (approximately 3 times the combined AUC in patients administered the RDD of 50 mg), and craniofacial malformations (cleft lip and cleft palate) were observed at ≥1 mg/kg/day (approximately 0.3 times the combined AUC in patients administered the RDD of 50 mg).

Sunitinib (0.3, 1, 3 mg/kg/day) was evaluated in a pre- and postnatal development study in pregnant rats. Maternal body weight gains were reduced during gestation and lactation at doses ≥1 mg/kg/day (approximately 0.5 times the combined AUC in patients administered the RDD of 50 mg). At 3 mg/kg/day (approximately 2 times the combined AUC in patients administered the RDD of 50 mg), reduced neonate body weights were observed at birth and persisted in the offspring of both sexes during the preweaning period and in males during postweaning period. No adverse developmental effects were observed at doses ≤1 mg/kg/day.

8.2 Lactation

There is no information regarding the presence of sunitinib and its metabolites in human milk. Sunitinib and its metabolites were excreted in rat milk at concentrations up to 12-fold higher than in plasma (see Data). Because of the potential for serious adverse reactions in breastfed infants, advise women not to breastfeed during treatment with SUTENT and for at least 4 weeks after the last dose.

Data

Animal Data

In lactating female rats administered 15 mg/kg, sunitinib and its metabolites were excreted in milk at concentrations up to 12-fold higher than in plasma.

8.3 Females and Males of Reproductive Potential

SUTENT can cause fetal harm when administered to a pregnant woman [see Use in Specific Populations (8.1)].

Pregnancy Testing

Verify pregnancy status of females of reproductive potential prior to initiating treatment with SUTENT.

Contraception

Females

Advise females of reproductive potential to use effective contraception during treatment with SUTENT and for at least 4 weeks after the last dose.

Males

Based on findings in animal reproduction studies, advise males with female partners of reproductive potential to use effective contraception during treatment with SUTENT and for 7 weeks after the last dose.

Infertility

Based on findings in animals, SUTENT may impair male and female fertility [see Nonclinical Toxicology (13.1)].

8.4 Pediatric Use

The safety and effectiveness of SUTENT in pediatric patients have not been established. Safety and pharmacokinetics of sunitinib were assessed in an open-label study (NCT00387920) in pediatric patients 2 years to <17 years of age (n=29) with refractory solid tumors. In addition, efficacy, safety and pharmacokinetics of sunitinib was assessed in another open-label study (NCT01462695) in pediatric patients 2 years to <17 years of age (n=27) with high-grade glioma or ependymoma. The maximum tolerated dose (MTD) normalized for body surface area (BSA) was lower in pediatric patients compared to adults. Sunitinib was poorly tolerated in pediatric patients. The occurrence of dose-limiting cardiotoxicity prompted an amendment of the NCT00387920 study to exclude patients with previous exposure to anthracyclines or cardiac radiation. No responses were reported in patients in either of the trials.

Apparent clearance and volume of distribution normalized for BSA for sunitinib and its active major metabolite were lower in pediatrics as compared to adults.

The effect on open tibial growth plates in pediatric patients who received SUTENT has not been adequately studied. See Juvenile Animal Toxicity Data below.

Juvenile Animal Toxicity Data

Physeal dysplasia was present in cynomolgus monkeys with open growth plates treated with sunitinib for ≥3 months (3 month dosing 2, 6, 12 mg/kg/day; 8 cycles of dosing 0.3, 1.5, 6.0 mg/kg/day) at doses that were >0.4 times the combined AUC (the combined systemic exposure of sunitinib plus its active metabolite) in patients administered the RDD of 50 mg. The no-effect level (NOEL) was 1.5 mg/kg/day in monkeys treated intermittently for 8 cycles, but was not identified in monkeys treated continuously for 3 months. In developing rats treated continuously for 3 months (1.5, 5.0, and 15.0 mg/kg) or 5 cycles (0.3, 1.5, and 6.0 mg/kg/day), bone abnormalities consisted of thickening of the epiphyseal cartilage of the femur and an increase of fracture of the tibia at doses ≥5 mg/kg (approximately 10 times the combined AUC in patients administered the RDD of 50 mg). Additionally, tooth caries were present in rats at >5 mg/kg. The incidence and severity of physeal dysplasia were dose related and reversible upon cessation of treatment; however, findings in the teeth were not. In rats, the NOEL in bones was ≤2 mg/kg/day.

8.5 Geriatric Use

Of the 7527 patients with GIST, RCC (advanced and adjuvant), or pNET who received SUTENT, 32% were 65 years and older, and 7% were 75 years and older. Patients aged 65 years of age and older had a higher incidence of Grade 3 or 4 adverse reactions (67%) than younger patients (60%).

In the GIST study, 73 (30%) of the patients who received SUTENT were 65 years and older. In the mRCC study, 152 (41%) of patients who received SUTENT were 65 years and older. No overall differences in safety or effectiveness were observed between these patients and younger patients.

In the pNET study, 22 (27%) of the patients who received SUTENT were 65 years and older. Clinical studies of SUTENT did not include sufficient numbers of patients with pNET to determine if patients 65 years of age and older respond differently than younger patients.

8.6 Hepatic Impairment

No dose adjustment is required in patients with mild or moderate (Child-Pugh Class A or B) hepatic impairment [see Clinical Pharmacology (12.3)]. SUTENT was not studied in patients with severe (Child-Pugh Class C) hepatic impairment.

8.7 Renal Impairment

No dose adjustment is recommended in patients with mild (CLcr 50 to 80 mL/min), moderate (CLcr 30 to <50 mL/min), or severe (CLcr <30 mL/min) renal impairment who are not on dialysis [see Clinical Pharmacology (12.3)].

No dose adjustment is recommended for patients with end-stage renal disease (ESRD) on hemodialysis [see Clinical Pharmacology (12.3)].

10 OVERDOSAGE

Treatment of overdose with SUTENT should consist of general supportive measures. There is no specific antidote for overdosage with SUTENT. If indicated, elimination of unabsorbed drug should be achieved by emesis or gastric lavage. Cases of accidental overdose have been reported; these cases were associated with adverse reactions consistent with the known safety profile of SUTENT, or without adverse reactions. In nonclinical studies, mortality was observed following as few as 5 daily doses of 500 mg/kg (3000 mg/m^2) in rats. At this dose, signs of toxicity included impaired muscle coordination, head shakes, hypoactivity, ocular discharge, piloerection, and gastrointestinal distress. Mortality and similar signs of toxicity were observed at lower doses when administered for longer durations.

11 DESCRIPTION

Sunitinib is a kinase inhibitor present in SUTENT capsules as the malate salt. Sunitinib malate is described chemically as (2S)-2-hydroxybutanedoic acid with N-[2-(diethylamino)ethyl]-5-[(Z)-(5-fluoro-1,2-dihydro-2-oxo-3H-indol-3-ylidine)methyl]-2,4-dimethyl-1H-pyrrole-3-carboxamide (1:1). The molecular formula is C22H27FN4O2 ∙ C4H6O5 and the molecular weight is 532.6 Daltons. The chemical structure of sunitinib malate is:

Sunitinib malate is a yellow to orange powder with a pKa of 8.95. The solubility of sunitinib malate in aqueous media over the range pH 1.2 to pH 6.8 is in excess of 25 mg/mL. The log of the distribution coefficient (octanol/water) at pH 7 is 5.2.

SUTENT (sunitinib malate) capsules are supplied as printed hard shell capsules containing 12.5 mg, 25 mg, 37.5 mg or 50 mg of sunitinib (equivalent to 16.7 mg, 33.4 mg, 50.1 mg, or 66.8 mg of sunitinib malate, respectively). The capsules contain the following inactive ingredients: croscarmellose sodium, magnesium stearate, mannitol, and povidone (K-25). The orange gelatin capsule shells contain titanium dioxide and red iron oxide; the caramel gelatin capsule shells contain titanium dioxide, red iron oxide, yellow iron oxide, and black iron oxide; and the yellow gelatin capsule shells contain titanium dioxide and yellow iron oxide. The white printing ink contains shellac, propylene glycol, sodium hydroxide, povidone, and titanium dioxide and the black printing ink contains shellac, propylene glycol, potassium hydroxide, and black iron oxide.

12 CLINICAL PHARMACOLOGY

12.1 Mechanism of Action

Sunitinib is a small molecule that inhibits multiple receptor tyrosine kinases (RTKs), some of which are implicated in tumor growth, pathologic angiogenesis, and metastatic progression of cancer. Sunitinib was evaluated for its inhibitory activity against a variety of kinases (>80 kinases) and was identified as an inhibitor of platelet-derived growth factor receptors (PDGFRα and PDGFRβ), vascular endothelial growth factor receptors (VEGFR1, VEGFR2, and VEGFR3), stem cell factor receptor (KIT), Fms-like tyrosine kinase-3 (FLT3), colony stimulating factor receptor Type 1 (CSF-1R), and the glial cell-line derived neurotrophic factor receptor (RET). Sunitinib inhibition of the activity of these RTKs has been demonstrated in biochemical and cellular assays, and inhibition of function has been demonstrated in cell proliferation assays. The primary metabolite exhibits similar potency compared to sunitinib in biochemical and cellular assays.

Sunitinib inhibited the phosphorylation of multiple RTKs (PDGFRβ, VEGFR2, KIT) in tumor xenografts expressing RTK targets in vivo and demonstrated inhibition of tumor growth or tumor regression and/or inhibited metastases in some experimental models of cancer. Sunitinib demonstrated the ability to inhibit growth of tumor cells expressing dysregulated target RTKs (PDGFR, RET, or KIT) in vitro and to inhibit PDGFRβ- and VEGFR2-dependent tumor angiogenesis in vivo.

12.2 Pharmacodynamics

Exposure-Response Relationship

Based on population pharmacokinetic/pharmacodynamic analyses, there were relationships between changes in different pharmacodynamic endpoints (i.e., safety and efficacy endpoints) over time and sunitinib plasma exposures.

Cardiac Electrophysiology

SUTENT can cause QT interval prolongation in a dose-dependent manner, which may lead to an increased risk for ventricular arrhythmias including Torsade de Pointes [see Warnings and Precautions (5.3)].

12.3 Pharmacokinetics

The pharmacokinetics of sunitinib and sunitinib malate have been evaluated in healthy subjects and in patients with solid tumors.

Sunitinib AUC and Cmax increase proportionately over a dose range of 25 mg to 100 mg (0.5 to 2 times the approved RDD of 50 mg). The pharmacokinetics were similar in healthy subjects and in patients with a solid tumor, including patients with GIST and RCC. No significant changes in the pharmacokinetics of sunitinib or the primary active metabolite were observed with repeated daily administration or with repeated cycles. With repeated daily administration, sunitinib accumulates 3- to 4-fold while the primary metabolite accumulates 7- to 10-fold. Steady-state concentrations of sunitinib and its primary active metabolite are achieved within 10 to 14 days. By Day 14, combined plasma concentrations of sunitinib and its active metabolite ranged from 63 to 101 ng/mL.

Absorption

Following oral administration of sunitinib, the time to maximum plasma concentration (Tmax) ranged from 6 to 12 hours.

Effect of Food

The administration of a single dose of SUTENT 50 mg with a high-fat, high-calorie meal (consisting of approximately 150 protein calories and 500 to 600 fat calories) in healthy subjects had no clinically significant effect on SUTENT or active metabolites exposure.

Distribution

The apparent volume of distribution (Vd/F) for sunitinib is 2230 L. Binding of sunitinib and its primary active metabolite to human plasma protein in vitro is 95% and 90%, respectively, with no concentration dependence in the range of 100 to 4000 ng/mL.

Elimination

Following administration of a single oral dose in healthy subjects, the terminal half-lives of sunitinib and its primary active metabolite are approximately 40 to 60 hours and 80 to 110 hours, respectively. Sunitinib total oral clearance (CL/F) ranged from 34 to 62 L/h with an interpatient variability of 40%.

Metabolism

Sunitinib is metabolized primarily by CYP3A4 to its primary active metabolite, which is further metabolized by CYP3A4. The primary active metabolite comprises 23% to 37% of the total exposure. After a radiolabeled dose, sunitinib and its active metabolite were the major compounds identified in plasma, accounting for 92% of radioactivity.

Excretion

After a radiolabeled dose of sunitinib, approximately 61% of the dose was recovered in feces and 16% in urine.

Sunitinib and its primary active metabolite were the major compounds identified in urine and feces, representing 86% and 74% of radioactivity, respectively.

Specific Populations

No clinically significant differences in the pharmacokinetics of sunitinib or the primary active metabolite were observed based on age (18 to 84 years), body weight (34 to 168 kg), race (White, Black, or Asian), sex, Eastern Cooperative Oncology Group (ECOG) score, mild (Child-Pugh Class A) or moderate (Child-Pugh Class B) hepatic impairment.

Patients with Renal Impairment

No clinically significant differences in the pharmacokinetics of sunitinib or its active metabolite were predicted or observed in patients with mild (CLcr 50 to 80 mL/min), moderate (CLcr 30 to <50 mL/min), or severe (CLcr <30 mL/min) renal impairment who are not on dialysis, compared to patients with normal renal function (CLcr >80 mL/min). Although sunitinib was not eliminated through hemodialysis, the sunitinib systemic exposure was 47% lower in patients with end stage renal disease (ESRD) on hemodialysis compared to patients with normal renal function.

Drug Interaction Studies

Clinical Studies

Effect of strong CYP3A4 inhibitors on sunitinib: Co-administration of a single SUTENT dose with ketoconazole (strong CYP3A4 inhibitor) increased the combined sunitinib and its active metabolite Cmax and AUC0–inf by 49% and 51%, respectively, in healthy subjects.

Effect of strong CYP3A4 inducers on sunitinib: Co-administration of a single SUTENT dose with rifampin (strong CYP3A4 inducer) reduced the combined sunitinib and its active metabolite Cmax and AUC0–inf by 23% and 46%, respectively in healthy subjects.

In Vitro Studies

In vitro studies in human hepatocytes and microsomes indicated that sunitinib and the primary active metabolite do not induce CYP1A2, CYP2E1, and CYP3A4/5, or inhibit CYP1A2, CYP2A6, CYP2B6, CYP2C8, CYP2C9, CYP2C19, CYP2D6, CYP2E1, CYP3A4/5, and CYP4A9/11 at clinically relevant concentrations.

13 NONCLINICAL TOXICOLOGY

13.1 Carcinogenesis, Mutagenesis, Impairment of Fertility

The carcinogenic potential of sunitinib has been evaluated in 2 species: rasH2 transgenic mice and Sprague-Dawley rats. There were similar positive findings in both species. In rasH2 transgenic mice, gastroduodenal carcinomas and/or gastric mucosal hyperplasia, as well as an increased incidence of background hemangiosarcomas were observed at sunitinib daily doses of ≥25 mg/kg/day in studies of 1 or 6 months duration. No proliferative changes were observed in rasH2 transgenic mice at 8 mg/kg/day. Similarly, in a 2-year rat carcinogenicity study, administration of sunitinib in 28-day cycles followed by 7-day dose-free periods resulted in findings of duodenal carcinoma at doses as low as 1 mg/kg/day [approximately 0.9 times the combined AUC (combined systemic exposure of sunitinib plus its active metabolite) in patients administered the RDD of 50 mg]. At the high dose of 3 mg/kg/day (approximately 8 times the combined AUC in patients administered the RDD of 50 mg), the incidence of duodenal tumors was increased and was accompanied by findings of gastric mucous cell hyperplasia and by an increased incidence of pheochromocytoma and hyperplasia of the adrenal gland.

Sunitinib did not cause genetic damage when tested in in vitro assays [bacterial mutation (Ames test), human lymphocyte chromosome aberration] and an in vivo rat bone marrow micronucleus test.

In a female fertility and early embryonic development study, female rats were administered oral sunitinib (0.5, 1.5, 5 mg/kg/day) for 21 days prior to mating and for 7 days after mating. Preimplantation loss was observed in females administered 5 mg/kg/day (approximately 5 times the combined AUC in patients administered the RDD of 50 mg). No adverse effects on fertility were observed at doses ≤1.5 mg/kg/day (approximately equal to the combined AUC in patients administered the RDD of 50 mg). In addition, effects on the female reproductive system were identified in a 3-month oral repeat-dose monkey study (2, 6, 12 mg/kg/day). Ovarian changes (decreased follicular development) were noted at 12 mg/kg/day (approximately 5 times the combined AUC in patients administered the RDD of 50 mg), while uterine changes (endometrial atrophy) were noted at ≥2 mg/kg/day (approximately 0.4 times the combined AUC in patients administered the RDD of 50 mg). With the addition of vaginal atrophy, the uterine and ovarian effects were reproduced at 6 mg/kg/day (approximately 0.8 times the combined AUC in patients administered the RDD of 50 mg) in a 9-month monkey study (0.3, 1.5, and 6 mg/kg/day administered daily for 28 days followed by a 14-day respite).

In a male fertility study, no reproductive effects were observed in male rats dosed with 1, 3, or 10 mg/kg/day oral sunitinib for 58 days prior to mating with untreated females. Fertility, copulation, conception indices, and sperm evaluation (morphology, concentration, and motility) were unaffected by sunitinib at doses ≤10 mg/kg/day (approximately ≥26 times the combined AUC in patients administered the RDD of 50 mg).

14 CLINICAL STUDIES

14.1 Gastrointestinal Stromal Tumor

Study 1

Study 1 (NCT#00075218) was a 2-arm, international, randomized, double-blind, placebo-controlled trial of SUTENT in patients with GIST who had disease progression during prior imatinib mesylate (imatinib) treatment or who were intolerant of imatinib. The objective was to compare time-to-tumor progression (TTP) in patients receiving SUTENT plus best supportive care versus patients receiving placebo plus best supportive care. Other objectives included progression-free survival (PFS), objective response rate (ORR), and overall survival (OS). Patients were randomized (2:1) to receive either 50 mg SUTENT or placebo orally, once daily, on Schedule 4/2 until disease progression or withdrawal from the study for another reason. Treatment was unblinded at the time of disease progression. Patients randomized to placebo were then offered crossover to open-label SUTENT and patients randomized to SUTENT were permitted to continue treatment per investigator judgment.

At the time of a prespecified interim analysis, the intent-to-treat (ITT) population included 312 patients. Two hundred seven (207) patients were randomized to the SUTENT arm and 105 patients were randomized to the placebo arm. Demographics were comparable between the SUTENT and placebo groups with regard to age (69% versus 72% <65 years for SUTENT versus placebo, respectively), sex (male: 64% versus 61%), race (White: 88% both arms, Asian: 5% both arms, Black: 4% both arms, remainder not reported), and performance status (ECOG 0: 44% versus 46%, ECOG 1: 55% versus 52%, and ECOG 2: 1% versus 2%). Prior treatment included surgery (94% versus 93%) and radiotherapy (8% versus 15%). Outcome of prior imatinib treatment was also comparable between arms with intolerance (4% versus 4%), progression within 6 months of starting treatment (17% versus 16%), or progression beyond 6 months (78% versus 80%) balanced.

The planned interim efficacy and safety analysis was performed after 149 TTP events had occurred. There was a statistically significant advantage for SUTENT over placebo in TTP, meeting the primary endpoint. Efficacy results are summarized in Table 10 and the Kaplan-Meier curve for TTP is shown in Figure 1.

Table 10. GIST Efficacy Results From Study 1 (Double-Blind Treatment Phase)
Efficacy Parameter | SUTENT (N=207) | Placebo (N=105) | p-value (log-rank test) | HR (95% CI)
Time-to-tumor progression [Time from randomization to progression; deaths prior to documented progression were censored at time of last radiographic evaluation.] [median, weeks (95% CI)] | 27.3 (16.0, 32.1) | 6.4 (4.4, 10.0) | <0.0001 [A comparison is considered statistically significant if the p-value is <0.00417 (O'Brien Fleming stopping boundary).] | 0.33 (0.23, 0.47)
Progression-free survival [Time from randomization to progression or death due to any cause.] [median, weeks (95% CI)] | 24.1 (11.1, 28.3) | 6.0 (4.4, 9.9) | <0.0001 | 0.33 (0.24, 0.47)
Objective response rate (PR) [%, (95% CI)] | 6.8 (3.7, 11.1) | 0 | 0.006 [Pearson chi-square test.]
Abbreviations: CI=confidence interval; GIST=gastrointestinal stromal tumor; HR=hazard ratio; N=number of patients; PR=partial response.

Figure 1. Kaplan-Meier Curve of TTP in GIST Study 1 (Intent-to-Treat Population)

Abbreviations: CI=confidence interval; GIST=gastrointestinal stromal tumor; N=number of patients; TTP=time-to-tumor progression.

The final ITT population enrolled in the double-blind treatment phase of the study included 243 patients randomized to the SUTENT arm and 118 patients randomized to the placebo arm. After the primary endpoint was met at the interim analysis, the study was unblinded, and patients on the placebo arm were offered open-label SUTENT treatment. Ninety-nine (99) of the patients initially randomized to placebo crossed over to receive SUTENT in the open-label treatment phase. At the protocol specified final analysis of OS, the median OS was 72.7 weeks for the SUTENT arm and 64.9 weeks for the placebo arm [hazard ratio (HR)=0.876, 95% confidence interval (CI) (0.679, 1.129)].

Study 2

Study 2 was an open-label, multi-center, single-arm, dose-escalation study conducted in patients with GIST following progression on, or intolerance to imatinib. Following identification of the recommended regimen (50 mg once daily on Schedule 4/2), 55 patients in this study received the 50 mg dose of SUTENT on treatment Schedule 4/2. Partial responses (PR) were observed in 5 of 55 patients (9.1% PR rate; 95% CI: 3.0%, 20.0%).

14.2 Renal Cell Carcinoma

Treatment-Naïve

Study 3 (NCT#00083889) was a multi-center, international, randomized study comparing single-agent SUTENT with interferon alfa was conducted in patients with treatment-naïve RCC. The objective was to compare PFS in patients receiving SUTENT versus patients receiving interferon alfa. Other endpoints included ORR, OS, and safety. Seven hundred fifty (750) patients were randomized (1:1) to receive either 50 mg SUTENT once daily on Schedule 4/2 or to receive interferon alfa administered subcutaneously at 9 million international units (MIU) 3 times a week. Patients were treated until disease progression or withdrawal from the study.

The ITT population included 750 patients, 375 randomized to SUTENT and 375 randomized to interferon alfa. Demographics were comparable between the SUTENT and interferon alfa groups with regard to age (59% versus 67% <65 years for SUTENT versus interferon alfa, respectively), sex (male: 71% versus 72%), race (White: 94% versus 91%, Asian: 2% versus 3%, Black: 1% versus 2%, remainder not reported), and performance status (ECOG 0: 62% versus 61%, ECOG 1: 38% each arm, ECOG 2: 0 versus 1%). Prior treatment included nephrectomy (91% versus 89%) and radiotherapy (14% each arm). The most common site of metastases present at screening was the lung (78% versus 80%, respectively), followed by the lymph nodes (58% versus 53%, respectively) and bone (30% each arm); the majority of the patients had multiple (2 or more) metastatic sites at baseline (80% versus 77%, respectively).

There was a statistically significant advantage for SUTENT over interferon alfa in the endpoint of PFS (see Table 11 and Figure 2). In the prespecified stratification factors of lactate dehydrogenase (LDH) (>1.5 ULN versus ≤1.5 ULN), ECOG performance status (0 versus 1), and prior nephrectomy (yes versus no), the hazard ratio favored SUTENT over interferon alfa. The ORR was higher in the SUTENT arm (see Table 11).

Table 11. Treatment-Naïve RCC Efficacy Results (Interim Analysis) from Study 3
Efficacy Parameter | SUTENT (N=375) | Interferon Alfa (N=375) | p-value (log-rank test) | HR (95% CI)
Progression-free survival [Assessed by blinded core radiology laboratory; 90 patients' scans had not been read at time of analysis.] [median, weeks (95% CI)] | 47.3 (42.6, 50.7) | 22.0 (16.4, 24.0) | <0.000001 [A comparison is considered statistically significant if the p-value is <0.0042 (O'Brien Fleming stopping boundary).] | 0.415 (0.320, 0.539)
Objective response rate [%, (95% CI)] | 27.5 (23.0, 32.3) | 5.3 (3.3, 8.1) | <0.001 [Pearson chi-square test.] | NA
Abbreviations: CI=confidence interval; HR=hazard ratio; N=number of patients; NA=not applicable; RCC=renal cell carcinoma.

Figure 2. Kaplan-Meier Curve of PFS in Treatment-Naïve RCC Study 3 (Intent-to-Treat Population)

Abbreviations: CI=confidence interval; IFN-α=interferon-alfa; N=number of patients; PFS=progression-free survival; RCC=renal cell carcinoma.

At the protocol-specified final analysis of OS, the median OS was 114.6 weeks for the SUTENT arm and 94.9 weeks for the interferon alfa arm (HR=0.821; 95% CI: 0.673, 1.001). The median OS for the interferon alfa arm includes 25 patients who discontinued interferon alfa treatment because of disease progression and crossed over to treatment with SUTENT as well as 121 patients (32%) on the interferon alfa arm who received post-study cancer treatment with SUTENT.

Cytokine-Refractory

The use of single-agent SUTENT in the treatment of cytokine-refractory RCC was investigated in 2 single-arm, multi-center studies. All patients enrolled into these studies experienced failure of prior cytokine-based therapy. In Study 4 (NCT#00077974), failure of prior cytokine therapy was based on radiographic evidence of disease progression defined by response evaluation criteria in solid tumors (RECIST) or World Health Organization (WHO) criteria during or within 9 months of completion of 1 cytokine therapy treatment (interferon alfa, interleukin-2, or interferon alfa plus interleukin-2; patients who were treated with interferon alfa alone must have received treatment for at least 28 days). In Study 5 (NCT#00054886), failure of prior cytokine therapy was defined as disease progression or unacceptable treatment-related toxicity. The endpoint for both studies was ORR. Duration of response (DR) was also evaluated.

One hundred and six patients (106) were enrolled into Study 4 and 63 patients were enrolled into Study 5. Patients received 50 mg SUTENT on Schedule 4/2. Therapy was continued until the patients met withdrawal criteria or had progressive disease. The baseline age, sex, race, and ECOG performance statuses of the patients were comparable between Studies 4 and 5. Approximately 86%–94% of patients in the 2 studies were White. Men comprised 65% of the pooled population. The median age was 57 years and ranged from 24 to 87 years in the studies. All patients had an ECOG performance status <2 at the screening visit.

The baseline malignancy and prior treatment history of the patients were comparable between Studies 4 and 5. Across the 2 studies, 95% of the pooled population of patients had at least some component of clear-cell histology. All patients in Study 4 were required to have a histological clear-cell component. Most patients enrolled in the studies (97% of the pooled population) had undergone nephrectomy; prior nephrectomy was required for patients enrolled in Study 4. All patients had received 1 previous cytokine regimen. Metastatic disease present at the time of study entry included lung metastases in 81% of patients. Liver metastases were more common in Study 4 (27% versus 16% in Study 5) and bone metastases were more common in Study 5 (51% versus 25% in Study 4); 52% of patients in the pooled population had at least 3 metastatic sites. Patients with known brain metastases or leptomeningeal disease were excluded from both studies.

The ORR and DR data from Studies 4 and 5 are provided in Table 12. There were 36 PRs in Study 4 as assessed by a core radiology laboratory for an ORR of 34.0% (95% CI: 25.0%, 43.8%). There were 23 PRs in Study 5 as assessed by the investigators for an ORR of 36.5% (95% CI: 24.7%, 49.6%). The majority (>90%) of objective disease responses were observed during the first 4 cycles; the latest reported response was observed in Cycle 10. DR data from Study 4 is premature as only 9 of 36 patients (25%) responding to treatment had experienced disease progression or died at the time of the data cutoff.

Table 12. Cytokine-Refractory RCC Efficacy Results from Study 4 and Study 5
Efficacy Parameter | Study 4 (N=106) | Study 5 (N=63)
Objective response rate [%, (95% CI)] | 34.0 [Assessed by blinded core radiology laboratory.] (25.0, 43.8) | 36.5 [Assessed by investigators.] (24.7, 49.6)
Duration of response [median, weeks (95% CI)] | NR [Data not mature enough to determine upper confidence limit.] (42.0,) | 54 (34.3, 70.1)
Abbreviations: CI=confidence interval; N=number of patients; NR=not reached; RCC=renal cell carcinoma.

Adjuvant Treatment

In the adjuvant treatment setting, SUTENT was investigated in S-TRAC (NCT#00375674), a multi-center, international, randomized, double-blind, placebo-controlled, trial in patients with high risk of recurrent RCC following nephrectomy. Patients were required to have clear cell histology and high risk of recurrence defined as ≥T3 and/or N+ tumors. Six hundred fifteen (615) patients were randomized 1:1 to receive either 50 mg SUTENT once daily on Schedule 4/2 or placebo. Patients were treated for 9 cycles (approximately 1 year), or until disease recurrence, unacceptable toxicity, or withdrawal of consent.

Demographics were generally comparable between the SUTENT and placebo arms with regard to age (median age 58 years), sex (73% male), and race (84% White, 12% Asian and 4% Other). At randomization, most patients had an ECOG performance status of 0 (74% SUTENT and 72% placebo). The remainder of the patients had an ECOG performance status of 1; 1 patient on SUTENT had a performance status of 2.

The major efficacy outcome measure was disease-free survival (DFS) in patients receiving SUTENT versus placebo as assessed by blinded independent central review (BICR). Overall survival was an additional endpoint. There was a statistically significant improvement in DFS in patients who were treated with SUTENT compared to placebo (Table 13 and Figure 3). Prespecified subgroup analyses are presented in Table 14. At the time of the DFS analysis, overall survival data were not mature, with 141/615 (23%) patient deaths.

Table 13. Disease-free Survival Results as Assessed by BICR in Adjuvant RCC (Intent to Treat Population) from S-TRAC
 | SUTENT N=309 | Placebo N=306 | p-value [P-value based on log-rank test stratified by University of California Los Angeles Integrated Staging System (UISS) prognostic group; HR based on a Cox proportional hazard model stratified by UISS prognostic group] | HR (95% CI)
Median DFS [years (95% CI)] | 6.8 (5.8, NR) | 5.6 (3.8, 6.6) | 0.03 | 0.76 (0.59, 0.98)
DFS Events | 113 (36.6%) | 144 (47.1%)
5 Year DFS Rate | 59.3% | 51.3%
Abbreviations: BICR=blinded independent central review; CI=confidence interval; DFS=disease-free survival; HR=hazard ratio; N=number of patients; RCC=renal cell carcinoma.

Table 14. Disease-free Survival by Baseline Disease Characteristics
 | Number of Events/ Total n/N |  | Median DFS [years (95% CI)] |  | HR [HR based on a Cox proportional hazards model] (95% CI)
 | SUTENT | Placebo | SUTENT | Placebo
T3 Intermediate [T3 Intermediate: T3, N0 or NX, M0, any Fuhrman's grade, ECOG PS 0 OR T3, N0 or NX, M0, Fuhrman's grade 1, ECOG PS ≥ 1] | 35/115 | 46/112 | NR (5.2, NR) | 6.4 (4.7, NR) | 0.82 (0.53, 1.28)
T3 High [T3 High: T3, N0 or NX, M0, Fuhrman's grade ≥ 2, ECOG PS ≥ 1] | 63/165 | 79/166 | 6.8 (5.0, NR) | 5.3 (2.9, NR) | 0.77 (0.55, 1.07)
T4/Node Positive [T4/Node Positive: T4, N0 or NX, M0, any Fuhrman's grade, any ECOG PS OR Any T, N1–2, M0, any Fuhrman's grade, any ECOG PS] | 15/29 | 19/28 | 3.5 (1.2, NR) | 1.7 (0.4, 3.0) | 0.62 (0.31, 1.23)
Abbreviations: CI=confidence interval; DFS=disease-free survival; HR=hazard ratio; N=number of patients; n=number of events; NR=not reached

Figure 3. Kaplan-Meier Curve of Disease-free Survival as Assessed by BICR (Intent-to-Treat Population)

Abbreviations: BICR=blinded independent central review; CI=confidence interval; N=number of patients.

14.3 Pancreatic Neuroendocrine Tumors

Study 6 (NCT#00428597) was a multi-center, international, randomized, double-blind, placebo-controlled study of single-agent SUTENT conducted in patients with unresectable pNET. Patients were required to have documented RECIST-defined disease progression within the prior 12 months and were randomized (1:1) to receive either 37.5 mg SUTENT (N=86) or placebo (N=85) once daily without a scheduled off-treatment period. The primary objective was to compare PFS in patients receiving SUTENT versus patients receiving placebo. Other endpoints included OS, ORR, and safety. Use of somatostatin analogs was allowed in the study.

Demographics were comparable between the SUTENT and placebo groups. Additionally, 49% of SUTENT patients had nonfunctioning tumors vs 52% of placebo patients, and 92% patients in both arms had liver metastases. A total of 66% of SUTENT patients received prior systemic therapy compared with 72% of placebo patients and 35% of SUTENT patients had received somatostatin analogs compared with 38% of placebo patients. Patients were treated until disease progression or withdrawal from the study. Upon disease progression or study closure, patients were offered access to SUTENT in a separate extension study.

As recommended by the Independent Data Monitoring Committee, the study was terminated prematurely prior to the prespecified interim analysis. This may have led to an overestimate of the magnitude of PFS effect. A clinically significant improvement for SUTENT over placebo in PFS was seen by both investigator and independent assessment. A hazard ratio favoring SUTENT was observed in all subgroups of baseline characteristics evaluated. OS data were not mature at the time of the analysis. There were 9 deaths in the SUTENT arm and 21 deaths in the placebo arm. A statistically significant difference in ORR favoring SUTENT over placebo was observed. Efficacy results are summarized in Table 15 and the Kaplan-Meier curve for PFS is in Figure 4.

Table 15. pNET Efficacy Results from Study 6
Efficacy Parameter | SUTENT (N=86) | Placebo (N=85) | p-value | HR (95% CI)
Progression-free survival [median, months (95% CI)] | 10.2 (7.4, 16.9) | 5.4 (3.4, 6.0) | 0.000146 [2-sided unstratified log-rank test.] | 0.427 (0.271, 0.673)
Objective response rate [%, (95% CI)] | 9.3 (3.2, 15.4) | 0 | 0.0066 [Fisher's Exact test.] | NA
Abbreviations: CI=confidence interval; HR=hazard ratio; N=number of patients; NA=not applicable; pNET=pancreatic neuroendocrine tumors.

Figure 4. Kaplan-Meier Curve of PFS in the pNET Study 6

Abbreviations: CI=confidence interval; N=number of patients; PFS=progression-free survival; pNET=pancreatic neuroendocrine tumors.

16 HOW SUPPLIED/STORAGE AND HANDLING

SUTENT 12.5 mg capsules are supplied as hard gelatin capsule with orange cap and orange body, printed with white ink “Pfizer” on the cap, “STN 12.5 mg” on the body:
Bottles of 28 capsules: NDC 0069-0550-38

SUTENT 25 mg capsules are supplied as hard gelatin capsule with caramel cap and orange body, printed with white ink “Pfizer” on the cap, “STN 25 mg” on the body:
Bottles of 28 capsules: NDC 0069-0770-38

SUTENT 37.5 mg capsules are supplied as hard gelatin capsule with yellow cap and yellow body, printed with black ink “Pfizer” on the cap, “STN 37.5 mg” on the body:
Bottles of 28 capsules: NDC 0069-0830-38

SUTENT 50 mg capsules are supplied as hard gelatin capsule with caramel cap and caramel body, printed with white ink “Pfizer” on the cap, “STN 50 mg” on the body:
Bottles of 28 capsules: NDC 0069-0980-38

STORAGE AND HANDLING

Store at 20°C to 25°C (68°F to 77°F); excursions permitted to 15°C to 30°C (59°F to 86°F) [see USP Controlled Room Temperature].

17 PATIENT COUNSELING INFORMATION

Advise the patient to read the FDA-approved patient labeling (Medication Guide).

Hepatotoxicity

Inform patients of the signs and symptoms of hepatotoxicity. Advise patients to contact their healthcare provider immediately for signs or symptoms of hepatotoxicity [see Warnings and Precautions (5.1)].

Cardiovascular Events

Advise patients to contact their healthcare provider if they develop symptoms of heart failure [see Warnings and Precautions (5.2)].

QT Prolongation and Torsade de Pointes

Inform patients of the signs and symptoms of QT prolongation. Advise patients to contact their healthcare provider immediately in the event of syncope, pre-syncopal symptoms, and cardiac palpitations [see Warnings and Precautions (5.3)].

Hypertension

Inform patients of the signs and symptoms of hypertension. Advise patients to undergo routine blood pressure monitoring and to contact their health care provider if blood pressure is elevated or if they experience signs or symptoms of hypertension [see Warnings and Precautions (5.4)].

Hemorrhagic Events

Advise patients that SUTENT can cause severe bleeding. Advise patients to immediately contact their healthcare provider for bleeding or symptoms of bleeding [see Warnings and Precautions (5.5)].

Gastrointestinal Disorders

Advise patients that gastrointestinal disorders such as diarrhea, nausea, vomiting, and constipation may develop during SUTENT treatment and to seek immediate medical attention if they experience persistent or severe abdominal pain because cases of gastrointestinal perforation and fistula have been reported in patients taking SUTENT [see Warnings and Precautions (5.5), Adverse Reactions (6.1)].

Dermatologic Effects and Toxicities

Advise patients that depigmentation of the hair or skin may occur during treatment with SUTENT due to the drug color (yellow). Other possible dermatologic effects may include dryness, thickness or cracking of skin, blister or rash on the palms of the hands and soles of the feet. Severe dermatologic toxicities including Stevens-Johnson syndrome, Toxic Epidermal Necrolysis, erythema multiforme, and necrotizing fasciitis have been reported. Advise patients to immediately inform their healthcare provider if severe dermatologic reactions occur [see Warnings and Precautions (5.9), Adverse Reactions (6.1)].

Reversible Posterior Leukoencephalopathy Syndrome

Inform patients of the signs and symptoms of reversible posterior leukoencephalopathy syndrome. Advise patients to contact their healthcare provider if they develop symptoms of reversible posterior leukoencephalopathy syndrome [see Warnings and Precautions (5.10)].

Thyroid Dysfunction

Advise patients that SUTENT can cause thyroid dysfunction. Advise patient to contact their healthcare provider if symptoms of abnormal thyroid function occur [see Warnings and Precautions (5.11)].

Hypoglycemia

Advise patients that SUTENT can cause severe hypoglycemia and may be more severe in patients with diabetes taking antidiabetic medications. Inform patients of the signs, symptoms, and risks associated with hypoglycemia. Advise patients to immediately inform their healthcare provider if severe signs or symptoms of hypoglycemia occur [see Warnings and Precautions (5.12)].

Osteonecrosis of the Jaw

Advise patients regarding good oral hygiene practices and to inform their healthcare provider of any planned dental procedures. Advise patients to immediately contact their healthcare provider for signs or symptoms associated with osteonecrosis of the jaw [see Warnings and Precautions (5.13)].

Impaired Wound Healing

Advise patients that SUTENT impairs wound healing. Advise patients to inform their healthcare provider of any planned surgical procedures [see Warnings and Precautions (5.14)].

Concomitant Medications

Advise patients to inform their healthcare providers of all concomitant medications, including over-the-counter medications and dietary supplements [see Drug Interactions (7)].

Embryo-Fetal Toxicity

Advise pregnant women of the potential risk to a fetus. Advise females of reproductive potential to inform their healthcare provider of a known or suspected pregnancy [see Warnings and Precautions (5.15), Use in Specific Populations (8.1)].

Advise females of reproductive potential to use effective contraception during treatment and for 4 weeks after receiving the last dose of SUTENT [see Use in Specific Populations (8.3)].

Advise males with female partners of reproductive potential to use effective contraception during treatment and for 7 weeks after receiving the last dose of SUTENT [see Use in Specific Populations (8.3)].

Lactation

Advise women not to breastfeed during treatment with SUTENT and for at least 4 weeks after the last dose [see Use in Specific Populations (8.2)].

Infertility

Advise patients that SUTENT may impair male and female fertility [see Use in Specific Populations (8.3), Nonclinical Toxicology (13.1)].

Missed Dose

Advise patients that miss a dose of SUTENT by less than 12 hours to take the missed dose right away. Advise patients that miss a dose of SUTENT by more than 12 hours to take the next scheduled dose at its regular time.

This product’s labeling may have been updated. For the most recent prescribing information, please visit http://www.pfizer.com.

LAB-0317-29.0

MEDICATION GUIDE
SUTENT® (su TENT)
(sunitinib malate)
capsules

What is the most important information I should know about SUTENT?
SUTENT can cause serious side effects including:

- Severe liver problems, that can lead to death. Tell your healthcare provider right away if you develop any of the following signs and symptoms of liver problems during treatment with SUTENT:
  - itching
  - yellow eyes or skin
  - dark urine
  - pain or discomfort in the right upper stomach area

Your healthcare provider should do blood tests to check your liver function before you start taking and during treatment with SUTENT. Your healthcare provider may temporarily stop, reduce your dose, or permanently stop treatment with SUTENT if you develop liver problems.
See “What are the possible side effects of SUTENT?” for more information about side effects.

What is SUTENT?
SUTENT is a prescription medicine used to treat:

- a rare cancer of the stomach, bowel, or esophagus called gastrointestinal stromal tumor (GIST) and when:
  - you have taken the medicine imatinib mesylate and it did not stop the cancer from growing, or
  - you cannot take imatinib mesylate.
- advanced kidney cancer (advanced renal cell carcinoma or RCC).
- adults with kidney cancer that has not spread (localized), and who are at high risk of RCC coming back again after having kidney surgery.
- a type of pancreatic cancer called pancreatic neuroendocrine tumors (pNET), that has progressed and cannot be treated with surgery.

It is not known if SUTENT is safe and effective in children.

Before taking SUTENT tell your healthcare provider about all of your medical conditions, including if you:

- have any heart problems
- have high blood pressure
- have thyroid problems
- have a history of low blood sugar or diabetes
- have kidney function problems (other than cancer)
- have liver problems
- have any bleeding problem
- plan to have surgery or have had a recent surgery. You should stop taking SUTENT at least 3 weeks before planned surgery. See "What are the possible side effects of SUTENT?"
- have seizures
- have or have had pain in the mouth, teeth or jaw, swelling or sores inside the mouth, numbness or a feeling of heaviness in the jaw, or loosening of a tooth
- are pregnant or plan to become pregnant. SUTENT can harm your unborn baby.
  Females who are able to become pregnant:
  - Your healthcare provider should do a pregnancy test before you start treatment with SUTENT.
  - You should use effective birth control (contraception) during treatment and for at least 4 weeks after your last dose of SUTENT.
  - Tell your healthcare provider right away if you become pregnant or think you are pregnant during treatment with SUTENT.
Males with female partners who are able to become pregnant should use effective birth control (contraception) during treatment and for 7 weeks after your last dose of SUTENT.
  SUTENT may cause fertility problems in males and females. Tell your healthcare provider if this is a concern for you.
- are breastfeeding or plan to breastfeed. Do not breastfeed during treatment with SUTENT and for at least 4 weeks (1 month) after the last dose.

Tell all of your healthcare providers and dentists that you are taking SUTENT. They should talk to the healthcare provider who prescribed SUTENT for you, before you have any surgery, or medical or dental procedure.

Tell your healthcare provider about all the medicines you take, including prescription medicines and over-the-counter medicines, vitamins, and herbal supplements. Using SUTENT with certain other medicines can cause serious side effects.

You may have an increased risk of severe jawbone problems (osteonecrosis) if you take SUTENT and a bisphosphonate medicine. Especially tell your healthcare provider if you are taking or have taken an osteoporosis medicine.

Know the medicines you take. Keep a list of them to show your healthcare provider and pharmacist when you get a new medicine.

How should I take SUTENT?

- Take SUTENT exactly the way your healthcare provider tells you.
- Take SUTENT 1 time each day with or without food.
- If you take SUTENT for GIST or RCC, you will usually take your medicine for 4 weeks (28 days) and then stop for 2 weeks (14 days). This is 1 cycle of treatment. You will repeat this cycle for as long as your healthcare provider tells you to.
- If you take SUTENT for pNET, take it 1 time each day until your healthcare provider tells you to stop.
- Do not drink grapefruit juice or eat grapefruit during your treatment with SUTENT. They may cause you to have too much SUTENT in your body.
- Your healthcare provider may do blood tests before each cycle of treatment to check you for side effects.
- If you miss a dose of SUTENT by less than 12 hours, take the missed dose right away. If you miss a dose of SUTENT by more than 12 hours, just take your next dose at your regular time. Do not make up the missed dose. Tell your healthcare provider about any missed dose.
- Call your healthcare provider right away, if you take too much SUTENT.

What are possible side effects of SUTENT?
SUTENT may cause serious side effects, including:

- See “What is the most important information I should know about SUTENT?”
- Heart problems. Heart problems may include heart failure, heart attack and heart muscle problems (cardiomyopathy) that can lead to death. Tell your healthcare provider if you feel very tired, are short of breath, or have swollen feet and ankles.
- Abnormal heart rhythm changes. Changes in the electrical activity of your heart called QT prolongation can cause irregular heart beats that can be life threatening. Your healthcare provider may do electrocardiograms and blood tests (electrolytes) to watch for these problems during your treatment with SUTENT. Tell your healthcare provider right away if you feel dizzy, faint, or have abnormal heartbeats during your treatment with SUTENT

- you feel faint or lightheaded, or you pass out
- dizziness

- feel your heart beat is irregular or fast

- High blood pressure. High blood pressure is common with SUTENT and may sometimes be severe. Follow your healthcare provider’s instructions about having your blood pressure checked regularly. Call your healthcare provider if your blood pressure is high, or if you have any of the following signs or symptoms of high blood pressure:

- severe headache
- lightheadedness

- dizziness
- change in vision

Your healthcare provider may prescribe medicine for you to treat high blood pressure, if needed.

- Bleeding problems. Bleeding is common with SUTENT, but SUTENT can also cause severe bleeding problems that can lead to death. Your healthcare provider will monitor you for bleeding and may do blood tests if needed. Call your healthcare provider right away if you have any of these symptoms or a serious bleeding problem during treatment with SUTENT, including:

- painful, swollen stomach (abdomen)
- vomiting blood
- coughing up blood
- black, sticky stools

- bloody urine
- headache
- change in your mental status

- Serious stomach and intestinal problems, that can sometimes lead to death. Some people have had tears in their stomach or intestine (perforation), or have developed an abnormal opening between the stomach and intestine (fistula). Get medical help right away if you get stomach-area (abdominal) pain that does not go away or is severe during treatment with SUTENT.
- Tumor lysis syndrome (TLS). TLS is caused by the fast breakdown of cancer cells and may lead to death. TLS can cause kidney failure and the need for dialysis treatment, abnormal heart rhythm, seizure, and sometimes death. Your healthcare provider may do blood tests to check you for TLS.
- Abnormal changes in the brain (Reversible Posterior Leukoencephalopathy Syndrome [RPLS]). RPLS can cause a collection of symptoms including headache, confusion, and vision loss. Some people who have taken SUTENT have developed RPLS that can lead to death.
- Thrombotic microangiopathy (TMA) including thrombotic thrombocytopenia purpura (TTP) and hemolytic uremic syndrome (HUS). TMA is a condition that involves injury to the smallest blood vessels, and blood clots that can happen while taking SUTENT. TMA is accompanied by a decrease in red cells and cells that are involved with clotting. TMA may harm your body’s organs such as the brain and kidneys, and can sometimes lead to death.
- Protein in your urine. Some people who have taken SUTENT have developed protein in their urine, and in some cases, kidney problems that can lead to death. Your healthcare provider will check you for this problem.
- Serious skin and mouth reactions. Treatment with SUTENT has caused severe skin reactions that can lead to death, including:
  - severe rash with blisters or peeling of the skin.
  - painful sores or ulcers on the skin, lips or inside the mouth.
  - tissue damage (necrotizing fasciitis).
If you have any signs or symptoms of severe skin reactions, stop taking SUTENT and call your healthcare provider or get medical help right away.
- Thyroid problems. Your healthcare provider may do tests to check your thyroid function during SUTENT treatment. Tell your healthcare provider if you have any of the following signs and symptoms during your treatment with SUTENT:

- tiredness that gets worse and does not go away
- loss of appetite
- problems with heat
- feeling nervous or agitated, tremors
- sweating
- nausea or vomiting
- diarrhea

- fast heat rate
- weight gain or weight loss
- feeling depressed
- irregular menstrual periods or no menstrual periods
- headache
- hair loss

- Low blood sugar (hypoglycemia). Low blood sugar can happen with SUTENT, and may cause you to become unconscious, or you may need to be hospitalized. Low blood sugar with SUTENT may be worse in people who have diabetes and take antidiabetic medicines. Your healthcare provider should check your blood sugar levels regularly during treatment with SUTENT and may need to adjust the dose of your antidiabetic medicines. Call your healthcare provider right away if you have any of the following signs or symptoms of low blood sugar during your treatment with SUTENT:

- headache
- drowsiness
- weakness
- dizziness
- confusion

- irritability
- hunger
- fast heart beat
- sweating
- feeling jittery

- Jawbone problems (osteonecrosis). Severe jawbone problems have happened in some people who take SUTENT. Certain risk factors such as taking a bisphosphonate medicine or having dental disease may increase your risk of getting osteonecrosis. Your healthcare provider may tell you to see your dentist before you start taking SUTENT. Your healthcare provider may tell you to avoid dental procedures, if possible, during your treatment with SUTENT, especially if you are receiving a bisphosphonate medicine into a vein (intravenous). Tell your healthcare provider if you plan to have any dental procedures before or during treatment with SUTENT.
  - You should stop taking SUTENT at least 3 weeks before planned dental procedures.
  - Your healthcare provider should tell you when you may start taking SUTENT again after dental procedures.
- Wound healing problems. Wound healing problems have happened in some people who take SUTENT. Tell your healthcare provider if you plan to have any surgery before or during treatment with SUTENT.
  - You should stop taking SUTENT at least 3 weeks before planned surgery.
  - Your healthcare provider should tell you when you may start taking SUTENT again after surgery.

Your healthcare provider may temporarily stop, reduce your dose, or permanently stop treatment with SUTENT if you develop serious side effects.

Common side effects of SUTENT include:

- tiredness
- weakness
- diarrhea
- pain, swelling or sores inside of your mouth
- nausea
- loss of appetite
- indigestion

- vomiting
- stomach-area (abdominal) pain
- blisters or rash on the palms of your hands and soles of your feet
- high blood pressure
- taste changes
- low platelet counts

The medicine in SUTENT is yellow, and it may make your skin look yellow. Your skin and hair may get lighter in color. SUTENT may also cause other skin problems including: dryness, thickness or cracking of the skin.

These are not all of the possible side effects of SUTENT.

Call your doctor for medical advice about side effects. You may report side effects to FDA at 1-800-FDA-1088.

How do I store SUTENT?

- Store SUTENT at room temperature, between 68°F to 77°F (20°C to 25°C).

Keep SUTENT and all medicines out of the reach of children.

General information about the safe and effective use of SUTENT.

Medicines are sometimes prescribed for purposes other than those listed in a Medication Guide. Do not use SUTENT for a condition for which it was not prescribed. Do not give SUTENT to other people, even if they have the same symptoms that you have. It may harm them.

You can ask your healthcare provider or pharmacist for information about SUTENT that is written for health professionals.

What are the ingredients in SUTENT?
Active ingredient: sunitinib malate
Inactive ingredients: mannitol, croscarmellose sodium, povidone (K-25), and magnesium stearate.
Orange gelatin capsule shells: titanium dioxide, and red iron oxide.
Caramel gelatin capsule shells: titanium dioxide, red iron oxide, yellow iron oxide, and black iron oxide.
Yellow gelatin capsule shells: titanium dioxide and yellow iron oxide.
White printing ink: shellac, propylene glycol, sodium hydroxide, povidone, and titanium dioxide.
Black printing ink: shellac, propylene glycol, potassium hydroxide and black iron oxide.

LAB-0361-13.0
For more information go to www.SUTENT.com or call 1-877-5-SUTENT.

This Medication Guide has been approved by the U.S. Food and Drug Administration. Revised: October 2025

PRINCIPAL DISPLAY PANEL - 12.5 mg Capsule Bottle Label

ALWAYS DISPENSE WITH MEDICATION GUIDE

NDC 0069-0550-38

Pfizer

Sutent®
(sunitinib malate)

12.5 mg*

Capsules

28 Capsules
Rx only

PRINCIPAL DISPLAY PANEL - 25 mg Capsule Bottle Label

ALWAYS DISPENSE WITH MEDICATION GUIDE

NDC 0069-0770-38

Pfizer

Sutent®
(sunitinib malate)

25 mg*

Capsules

28 Capsules
Rx only

PRINCIPAL DISPLAY PANEL - 37.5 mg Capsule Bottle Label

ALWAYS DISPENSE WITH MEDICATION GUIDE

NDC 0069-0830-38

Pfizer

Sutent®
(sunitinib malate)

37.5 mg*

Capsules

28 Capsules
Rx only

PRINCIPAL DISPLAY PANEL - 50 mg Capsule Bottle Label

ALWAYS DISPENSE WITH MEDICATION GUIDE

NDC 0069-0980-38

Pfizer

Sutent®
(sunitinib malate)

50 mg*

Capsules

28 Capsules
Rx only